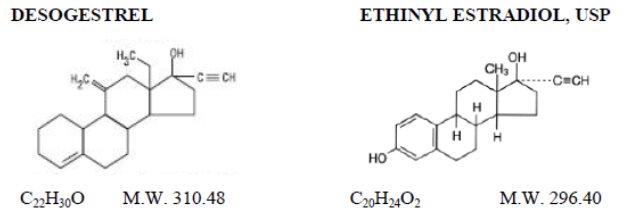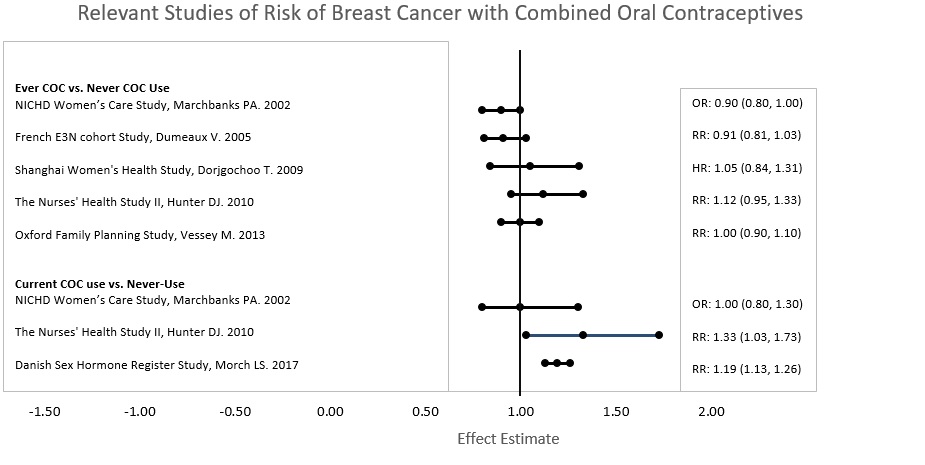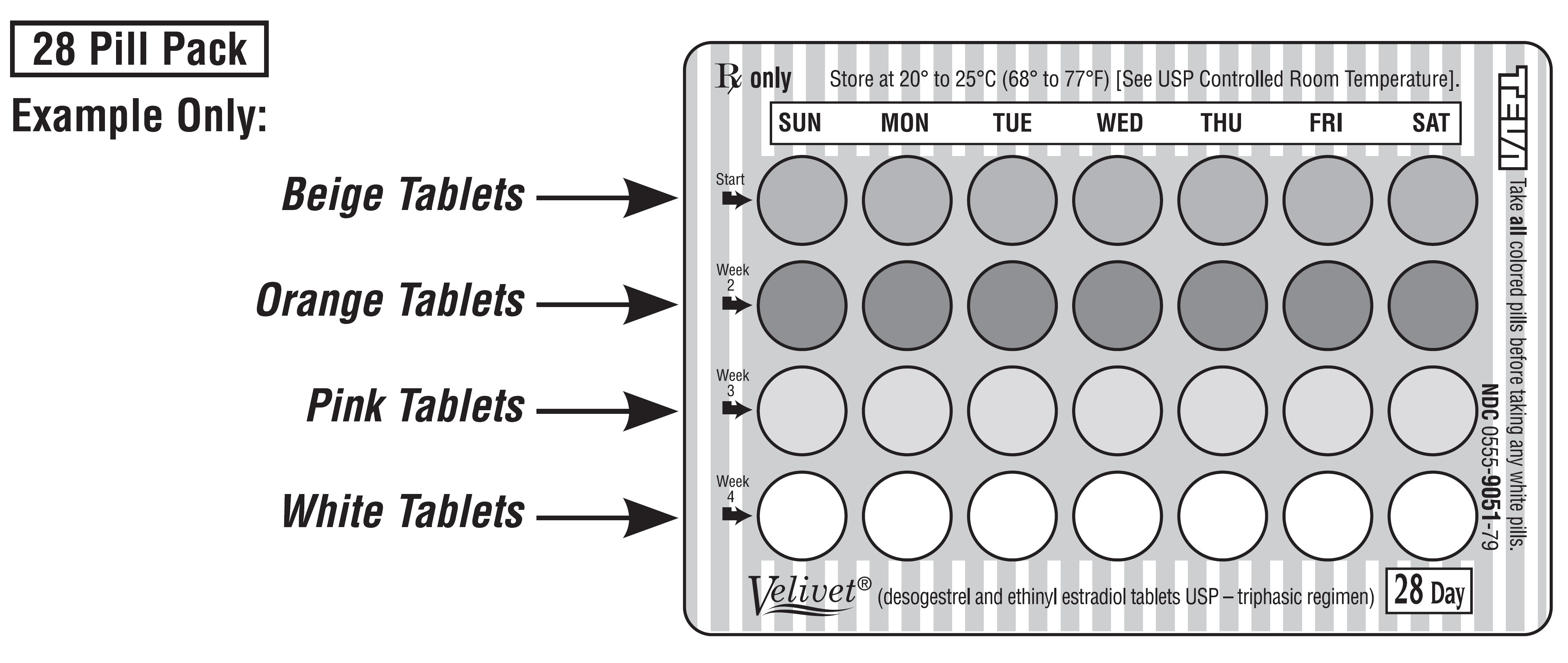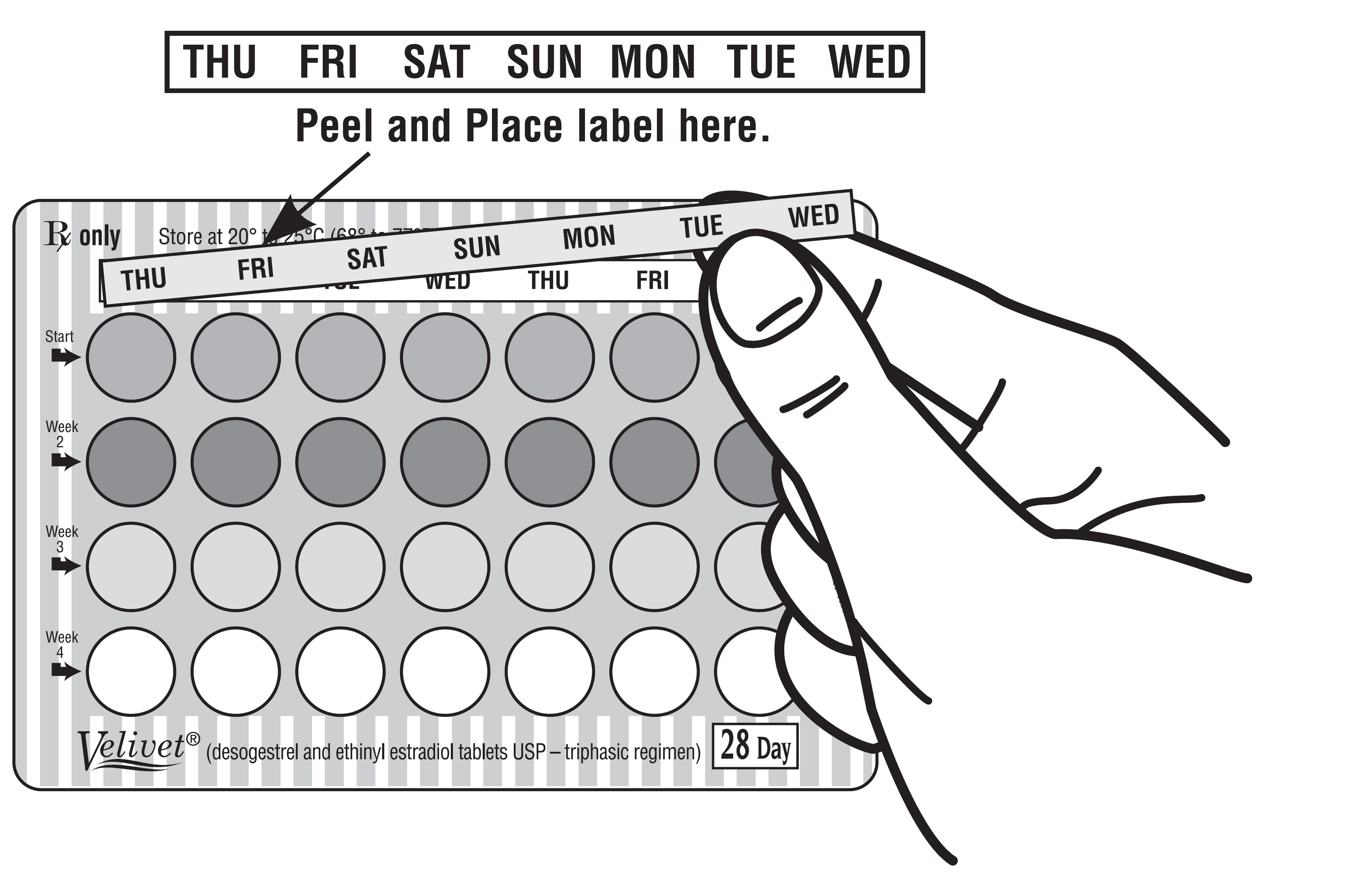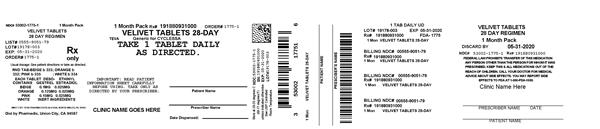 DRUG LABEL: Velivet
NDC: 53002-1775 | Form: KIT | Route: ORAL
Manufacturer: RPK Pharmaceuticals, Inc.
Category: prescription | Type: HUMAN PRESCRIPTION DRUG LABEL
Date: 20230607

ACTIVE INGREDIENTS: DESOGESTREL 0.1 mg/1 1; ETHINYL ESTRADIOL 0.025 mg/1 1
INACTIVE INGREDIENTS: SILICON DIOXIDE; HYPROMELLOSE 2910 (3 MPA.S); HYPROMELLOSE 2910 (6 MPA.S); LACTOSE MONOHYDRATE; POLYETHYLENE GLYCOL 400; POLYETHYLENE GLYCOL 8000; POLYSORBATE 80; POVIDONE K30; STARCH, CORN; STEARIC ACID; TITANIUM DIOXIDE; .ALPHA.-TOCOPHEROL; FERRIC OXIDE RED; FERRIC OXIDE YELLOW; FD&C RED NO. 40; FD&C YELLOW NO. 6; ANHYDROUS LACTOSE; MAGNESIUM STEARATE; MICROCRYSTALLINE CELLULOSE

Velivet®
(desogestrel and ethinyl estradiol tablets USP - triphasic regimen)
Patients should be counseled that this product does not protect against HIV infection (AIDS) and other sexually transmitted diseases.

DESCRIPTION

Velivet® (desogestrel and ethinyl estradiol tablets USP) is a triphasic oral contraceptive containing two active components, desogestrel and ethinyl estradiol, USP. Each 28 day treatment cycle pack consists of three active dosing phases: 7 beige tablets containing 0.1 mg desogestrel (13-ethyl-11-methylene-18,19-dinor-17α-pregn-4-en-20-yn-17-ol) and 0.025 mg ethinyl estradiol, USP (19-nor-17α-pregna-1,3,5(10)-trien-20-yne-3, 17-diol); 7 orange tablets containing 0.125 mg desogestrel and 0.025 mg ethinyl estradiol, USP, and 7 pink tablets containing 0.15 mg desogestrel and 0.025 mg ethinyl estradiol, USP. Inactive ingredients include colloidal silicon dioxide, hypromellose, lactose monohydrate, polyethylene glycol, polysorbate 80, povidone, pregelatinized corn starch, stearic acid, titanium dioxide and vitamin E. Beige tablets also contain iron oxide red and iron oxide yellow. Pink and orange tablets also contain FD&C Red No. 40 Aluminum Lake and FD&C Yellow No. 6 Aluminum Lake. Velivet also contains 7 white tablets with the following inert ingredients: lactose anhydrous, magnesium stearate, microcrystalline cellulose and pregelatinized corn starch. The structural formulas are as follows:

The 7 beige, 7 pink and 7 orange tablets meet Dissolution Test 2.

CLINICAL PHARMACOLOGY

Combination oral contraceptives act by suppression of gonadotropins. Although the primary mechanism of this action is inhibition of ovulation, other alterations include changes in the cervical mucus (which increase the difficulty of sperm entry into the uterus) and the endometrium (which reduce the likelihood of implantation).

Receptor-binding studies, as well as studies in animals, have shown that etonogestrel, the biologically active metabolite of desogestrel, combines high progestational activity with minimal intrinsic androgenicity.^(91, 92) The relevance of this latter finding in humans is unknown.

Pharmacokinetics

Absorption

Desogestrel is rapidly and almost completely absorbed and converted into etonogestrel, its biologically active metabolite. Following oral administration, the relative bioavailability of desogestrel, based on the lowest and highest tablet strengths, 0.100 mg desogestrel/0.025 mg ethinyl estradiol and 0.150 mg desogestrel/0.025 mg ethinyl estradiol, compared to solution, as measured by serum levels of etonogestrel, is approximately 100%. Ethinyl estradiol is rapidly and almost completely absorbed. When the lowest and highest tablet strengths, 0.100 mg desogestrel/0.025 mg ethinyl estradiol and 0.150 mg desogestrel/0.025 mg ethinyl estradiol, were compared to solution, the relative bioavailability of ethinyl estradiol was 92% and 98%, respectively. The effect of food on the bioavailability of desogestrel and ethinyl estradiol tablets following oral administration has not been evaluated.

The pharmacokinetics of etonogestrel and ethinyl estradiol following multiple dose administration of desogestrel and ethinyl estradiol tablets were determined during the third cycle in 21 subjects. After multiple dosing with desogestrel and ethinyl estradiol tablets, plasma concentrations of etonogestrel reached steady-state after four days of treatment during dosing Phases 1 and 3. During dosing Phase 2, steady-state was reached after five days of treatment. The dose-normalized AUC0 - 24 for etonogestrel was increased approximately 20% from Phase 1 to Phase 2 and approximately 10% from Phase 2 to Phase 3. SHBG concentrations were shown to be induced by the daily administration of ethinyl estradiol. Steady state for ethinyl estradiol was reached after four days of dosing in all dosing phases. The pharmacokinetic parameters of etonogestrel and ethinyl estradiol during the third cycle following multiple dose administration of desogestrel and ethinyl estradiol tablets are summarized in Table 1.

TABLE 1: MEAN (SD) PHARMACOKINETIC PARAMETERS OF DESOGESTREL AND ETHINYL ESTRADIOL TABLETS OVER A 28-DAY DOSING PERIOD IN THE THIRD CYCLE (n = 21).
Etonogestrel
Phase | Dose* | Cmax | tmax | n-AUC0-24 | CL/F
(days) | mg | pg/mL | hr | pg•hr/mL/mcg | L/hr
1 (1 to 7) | 0.100 | 2163.3 (856.4) | 1.6 (0.7) | 196.0 (75.4) | 6.1 (2.3)
2 (8 to 14) | 0.125 | 3241.5 (1296.5)† | 1.1 (0.3)† | 234.4 (85)† | 5.1 (1.9)†
3 (15 to 21) | 0.150 | 3855.7 (1273.1) | 1.5 (0.8) | 256.6 (104) | 4.6 (1.6)
Ethinyl Estradiol
Phase | Dose | Cmax | tmax | n-AUC0-24 | CL/F
(days) | mg | pg/mL | hr | pg•hr/mL/mcg | L/hr
1 (1 to 7) | 0.025 | 85.4 (51.7) | 1.5 (0.8) | 26.4 (11.5) | 43.5 (15)
2 (8 to 14) | 0.025 | 91.3 (52.2)† | 1.2 (1.2)† | 29 (15.5)† | 41.7 (15.5)†
3 (15 to 21) | 0.025 | 90.1 (48.2) | 1.2 (0.7) | 28.3 (13.2) | 42.5 (18.7)
Cmax – maximum serum drug concentration
tmax – time at which maximum serum drug concentration occurs
n-AUC0-24 – area under the concentration- vs. time curve -0 to 24 hours normalized to 1 mcg administered
CL/F – apparent clearance
Note: for information on t1/2 for Day 21, see the Excretion section.
* Desogestrel
† n = 20

Distribution

Etonogestrel, the active metabolite of desogestrel, was found to be 98% protein bound, primarily to sex hormone-binding globulin (SHBG). Ethinyl estradiol is primarily bound to plasma albumin. Ethinyl estradiol does not bind to SHBG, but induces SHBG synthesis. Desogestrel, in combination with ethinyl estradiol, does not counteract the estrogen-induced increase in SHBG, resulting in lower serum levels of free testosterone.96 to 99

Metabolism

Desogestrel
Desogestrel is rapidly and completely metabolized by hydroxylation in the intestinal mucosa and on first pass through the liver to etonogestrel. In vitro data suggest an important role for the cytochrome P450 CYP2C9 in the bioactivation of desogestrel. Further metabolism of etonogestrel into 6β-hydroxy, etonogestrel and 6β-13ethyl-dihydroxylated metabolites as major metabolites is catalyzed by CYP3A4. Other metabolites (i.e., 3α-OH-desogestrel, 3β-OH-desogestrel, and 3α-OH-5α-H-desogestrel) also have been identified and these metabolites may undergo glucuronide and sulfate conjugation.

Ethinyl Estradiol
Ethinyl estradiol is subject to a significant degree of presystemic conjugation (phase II metabolism). Ethinyl estradiol, escaping gut wall conjugation, undergoes phase I metabolism and hepatic conjugation (phase II metabolism). Major phase I metabolites are 2-OH-ethinyl estradiol and 2-methoxy-ethinyl estradiol. Sulfate and glucuronide conjugates of both ethinyl estradiol and phase I metabolites, which are excreted in bile, can undergo enterohepatic circulation.

Excretion

Etonogestrel and ethinyl estradiol are primarily eliminated in urine, bile and feces. At steady state, on Day 21, the elimination half-lives of etonogestrel and ethinyl estradiol are 37.1 ± 14.8 hours and 28.2 ± 10.5 hours, respectively.

Special Populations

Race

There is no information to determine the effect of race on the pharmacokinetics of desogestrel and ethinyl estradiol tablets.

Hepatic Insufficiency

No formal studies were conducted to evaluate the effect of hepatic disease on the disposition of desogestrel and ethinyl estradiol tablets. However, steroid hormones may be poorly metabolized in patients with impaired liver function (see PRECAUTIONS).

Renal Insufficiency

No formal studies were conducted to evaluate the effect of renal disease on the disposition of desogestrel and ethinyl estradiol tablets.

Drug-Drug Interactions

Interactions between desogestrel/ethinyl estradiol and other drugs have been reported in the literature. No formal drug-drug interaction studies were conducted with desogestrel and ethinyl estradiol tablets (see PRECAUTIONS).

INDICATIONS AND USAGE

Velivet (desogestrel and ethinyl estradiol tablets) is indicated for the prevention of pregnancy in women who elect to use this product as a method of contraception.

Oral contraceptives are highly effective. Table 2 lists the typical unintended pregnancy rates for users of combination oral contraceptives and other methods of contraception. The efficacy of these contraceptive methods, except sterilization, the IUD, and implants, depends upon the reliability with which they are used. Correct and consistent use of these methods can result in lower failure rates.

TABLE 2: PERCENTAGE OF WOMEN EXPERIENCING AN UNINTENDED PREGNANCY DURING THE FIRST YEAR OF TYPICAL USE AND THE FIRST YEAR OF PERFECT USE OF CONTRACEPTION AND THE PERCENTAGE CONTINUING USE AT THE END OF THE FIRST YEAR, UNITED STATES.
 | % of Women Experiencing an Unintended Pregnancy within the First Year of Use |  | % of Women Continuing Use at One Year*
Method | Typical Use† | Perfect Use‡
(1) | (2) | (3) | (4)
Chance§ | 85 | 85
Spermicides¶ | 26 | 6 | 40
Periodic abstinence | 25 |  | 63
Calendar |  | 9
Ovulation Method |  | 3
Sympto-Thermal# |  | 2
Post-Ovulation |  | 1
Withdrawal | 19 | 4
CapÞ
Parous Women | 40 | 26 | 42
Nulliparous Women | 20 | 9 | 56
Sponge
Parous Women | 40 | 20 | 42
Nulliparous Women | 20 | 9 | 56
DiaphragmÞ | 20 | 6 | 56
Condomβ
Female (Reality) | 21 | 5 | 56
Male | 14 | 3 | 61
Pill | 5 |  | 71
Progestin Only |  | 0.5
Combined |  | 0.1
IUD
Progesterone T | 2.0 | 1.5 | 81
Copper T 380A | 0.8 | 0.6 | 78
LNg 20 | 0.1 | 0.1 | 81
Depo-Provera | 0.3 | 0.3 | 70
Norplant and Norplant-2 | 0.05 | 0.05 | 88
Female sterilization | 0.5 | 0.5 | 100
Male sterilization | 0.15 | 0.10 | 100
Emergency Contraceptive Pills: Treatment initiated within 72 hours after unprotected intercourse reduces risk of pregnancy by at least 75%.à
Lactational Amenorrhea Method: LAM is a highly effective, temporary method of contraception. è
Source: Trussell J, Stewart F, Contraceptive Efficacy. In Hatcher RA, Trussell J, Stewart F, Cates W, Stewart GK, Kowal D, Guest F, Contraceptive Technology: Seventeenth Revised Edition. New York, NY: Irvington Publishers, 1998.
* Among couples attempting to avoid pregnancy, the percentage who continue to use a method for one year
† Among typical couples who initiate use of a method (not necessarily for the first time), the percentage who experience an accidental pregnancy during the first year if they do not stop use for any other reason
‡ Among couples who initiate use of a method (not necessarily for the first time) and who use it perfectly (both consistently and correctly), the percentage who experience an accidental pregnancy during the first year if they do not stop use for any other reason
à The treatment schedule is one dose within 72 hours after unprotected intercourse and a second dose 12 hours after the first dose. The Food and Drug Administration has declared the following brands of oral contraceptives to be safe and effective for emergency contraception: Ovral® (1 dose is 2 white pills), Alesse® (1 dose is 5 pink pills), Nordette® or Levlen® (1 dose is 2 light orange pills), Lo/Ovral® (1 dose is 4 white pills), Triphasil® or Tri-Levlen® (1 dose is 4 yellow pills)
è However, to maintain effective protection against pregnancy, another method of contraception must be used as soon as menstruation resumes, the frequency or duration of breastfeeds is reduced, bottle feeds are introduced or the baby reaches six months of age
§ The percentage of women becoming pregnant noted in columns (2) and (3) are based on data from populations where contraception is not used and from women who cease using contraception in order to become pregnant. Among such populations, about 89% became pregnant in one year. This estimate was lowered slightly (to 85%) to represent the percentage that would become pregnant within one year among women now relying on reversible methods of contraception if they abandon contraception altogether
¶ Foams, creams, gels, vaginal suppositories and vaginal film
# Cervical mucous (ovulation) method supplemented by calendar in the preovulatory and basal body temperature in the postovulatory phases
Þ With spermicidal cream or jelly
β Without spermicides

CONTRAINDICATIONS

Oral contraceptives should not be used in women who currently have the following conditions:

- Thrombophlebitis or thromboembolic disorders
- A past history of deep vein thrombophlebitis or thromboembolic disorders
- Cerebral vascular or coronary artery disease (current or history)
- Valvular heart disease with thrombogenic complications
- Severe hypertension
- Diabetes with vascular involvement
- Headaches with focal neurological symptoms
- Major surgery with prolonged immobilization
- Current diagnosis of, or history of, breast cancer, which may be hormone-sensitive
- Undiagnosed abnormal genital bleeding
- Cholestatic jaundice of pregnancy or jaundice with prior hormonal contraceptive use
- Hepatic tumors (benign or malignant) or active liver disease
- Known or suspected pregnancy
- Heavy smoking (≥ 15 cigarettes per day) and over age 35
- Hypersensitivity to any of the components of Velivet (desogestrel and ethinyl estradiol tablets)
- Are receiving Hepatitis C drug combinations containing ombitasvir/paritaprevir/ritonavir, with or without dasabuvir, due to the potential for ALT elevations (see WARNINGS, Risk of Liver Enzyme Elevations with Concomitant Hepatitis C Treatment).

WARNINGS

BOXED WARNING

Cigarette smoking increases the risk of serious cardiovascular side effects from oral contraceptive use. This risk increases with age and with heavy smoking (15 or more cigarettes per day) and is quite marked in women over 35 years of age. Women who use oral contraceptives should be strongly advised not to smoke.

The use of oral contraceptives is associated with increased risks of several serious conditions including venous and arterial thrombotic and thromboembolic events (such as myocardial infarction, thromboembolism, and stroke) hepatic neoplasia, gallbladder disease, and hypertension, although the risk of serious morbidity or mortality is very small in healthy women without underlying risk factors. The risk of morbidity and mortality increases significantly in the presence of other underlying risk factors such as certain inherited thrombophilias, hypertension, hyperlipidemias, obesity, and diabetes.

Practitioners prescribing oral contraceptives should be familiar with the following information relating to these risks.

The information contained in this package insert is principally based on studies carried out in patients who used oral contraceptives with formulations of higher doses of estrogens and progestogens than those in common use today. The effect of long-term use of the oral contraceptives with formulations of lower doses of both estrogens and progestogens remains to be determined.

Throughout this labeling, epidemiologic studies reported are of two types: retrospective or case control studies and prospective or cohort studies. Case control studies provide a measure of the relative risk of a disease, namely, a ratio of the incidence of a disease among oral contraceptive users to that among non-users. The relative risk does not provide information on the actual clinical occurrence of a disease. Cohort studies provide a measure of attributable risk, which is the difference in the incidence of disease between oral contraceptive users and non-users. The attributable risk does provide information about the actual occurrence of a disease in the population (Adapted from refs. 2 and 3 with the authors’ permission). For further information, the reader is referred to a text on epidemiological methods.

1. Thromboembolic Disorders and Other Vascular Problems

a. Thromboembolism

An increased risk of thromboembolic and thrombotic disease associated with the use of oral contraceptives is well established. Case control studies have found the relative risk of users compared to non-users to be 3 for the first episode of superficial venous thrombosis, 4 to 11 for deep vein thrombosis or pulmonary embolism, and 1.5 to 6 for women with predisposing conditions for venous thromboembolic disease.2, 3, 19 to 24 Cohort studies have shown the relative risk to be somewhat lower, about 3 for new cases and about 4.5 for new cases requiring hospitalization.^25 The risk of thromboembolic disease associated with oral contraceptives is not related to length of use and disappears after pill use is stopped.^2

Several epidemiologic studies indicate that third generation oral contraceptives, including those containing desogestrel, are associated with a higher risk of venous thromboembolism than certain second generation oral contraceptives.102 to 104 In general, these studies indicate an approximate two-fold increased risk, which corresponds to an additional 1 to 2 cases of venous thromboembolism per 10,000 women-years of use. However, data from additional studies have not shown this two-fold increase in risk.

A two- to four-fold increase in relative risk of post-operative thromboembolic complications has been reported with the use of oral contraceptives.^(9, 26) The relative risk of venous thrombosis in women who have predisposing conditions is twice that of women without such medical conditions.^(9, 26) If feasible, oral contraceptives should be discontinued at least four weeks prior to and for two weeks after elective surgery of a type associated with an increase in risk of thromboembolism and during and following prolonged immobilization. Since the immediate postpartum period is associated with an increased risk of thromboembolism, oral contraceptives should be started no earlier than four to six weeks after delivery in women who elect not to breastfeed.

b. Myocardial infarction

An increased risk of myocardial infarction has been attributed to oral contraceptive use. This risk is primarily in smokers or women with other underlying risk factors for coronary artery disease such as hypertension, hypercholesterolemia, morbid obesity, and diabetes. The relative risk of heart attack for current oral contraceptive users has been estimated to be two to six.4 to 10 The risk is very low in women under the age of 30.

Smoking in combination with oral contraceptive use has been shown to contribute substantially to the incidence of myocardial infarction in women in their mid-thirties or older with smoking accounting for the majority of excess cases.^11 Mortality rates associated with circulatory disease have been shown to increase substantially in smokers over the age of 35 and non-smokers over the age of 40 (Table 3) among women who use oral contraceptives.

TABLE 3: CIRCULATORY DISEASE MORTALITY RATES PER 100,000 WOMAN-YEARS BY AGE, SMOKING STATUS, AND ORAL CONTRACEPTIVE USE.
AGE | EVER-USERS NON-SMOKERS | EVER-USERS SMOKERS | CONTROLS NON-SMOKERS | CONTROLS SMOKERS
15 to 24 | 0 | 10.5 | 0 | 0
25 to 34 | 4.4 | 14.2 | 2.7 | 4.2
35 to 44 | 21.5 | 63.4 | 6.4 | 15.2
45+ | 52.4 | 206.7 | 11.4 | 27.9
Adapted from P.M. Layde and V. Beral, ref. #12.

Oral contraceptives may compound the effects of well-known risk factors, such as hypertension, diabetes, hyperlipidemias, age, and obesity.^13 In particular, some progestogens are known to decrease HDL cholesterol and cause glucose intolerance, while estrogens may create a state of hyperinsulinism.14 to 18 Oral contraceptives have been shown to increase blood pressure among users (see section 10 in WARNINGS). Similar effects on risk factors have been associated with an increased risk of heart disease. Oral contraceptives must be used with caution in women with cardiovascular disease risk factors.

c. Cerebrovascular diseases

Oral contraceptives have been shown to increase both the relative and attributable risks of cerebrovascular events (thrombotic and hemorrhagic strokes), although, in general, the risk is greatest among older (> 35 years), hypertensive women who also smoke. Hypertension was found to be a risk factor for both users and non-users, for both types of strokes, while smoking interacted to increase the risk for hemorrhagic strokes.27 to 29

In a large study, the relative risk of thrombotic strokes has been shown to range from 3 for normotensive users to 14 for users with severe hypertension.^30 The relative risk of hemorrhagic stroke is reported to be 1.2 for non-smokers who used oral contraceptives, 2.6 for smokers who did not use oral contraceptives, 7.6 for smokers who used oral contraceptives, 1.8 for normotensive users, and 25.7 for users with severe hypertension.^30 The attributable risk is also greater in older women.^3 Oral contraceptives also increase the risk for stroke in women with other underlying risk factors such as certain inherited or acquired thrombophilias, hyperlipidemias, and obesity. Women with migraine (particularly migraine with aura) who take combination oral contraceptives may be at an increased risk of stroke.

d. Dose-related risk of vascular disease from oral contraceptives

A positive association has been observed between the amount of estrogen and progestogen in oral contraceptives and the risk of vascular disease.31 to 33 A decline in serum high-density lipoproteins (HDL) has been reported with many progestational agents.14 to 16 A decline in serum high-density lipoproteins has been associated with an increased incidence of ischemic heart disease. Because estrogens increase HDL cholesterol, the net effect of an oral contraceptive depends on a balance achieved between doses of estrogen and progestogen and the nature and absolute amount of progestogens used in the contraceptives. The amount of both hormones should be considered in the choice of an oral contraceptive.

Minimizing exposure to estrogen and progestogen is in keeping with good principles of therapeutics. For any particular estrogen/progestogen combination, the dosage regimen prescribed should be one which contains the least amount of estrogen and progestogen that is compatible with a low failure rate and the needs of the individual patient. New acceptors of oral contraceptive agents should be started on a product containing the lowest hormone content that provides satisfactory results in the individual.

e. Persistence of risk of vascular disease

There are two studies which have shown persistence of risk of vascular disease for ever-users of oral contraceptives. In a study in the United States, the risk of developing myocardial infarction after discontinuing oral contraceptives persists for at least 9 years for women 40 to 49 years old who had used oral contraceptives for five or more years, but this increased risk was not demonstrated in other age groups.^8 In another study in Great Britain, the risk of developing cerebrovascular disease persisted for at least 6 years after discontinuation of oral contraceptives, although excess risk was very small.^34 However, both studies were performed with oral contraceptive formulations containing 50 micrograms or more of estrogens.

2. Estimates of Mortality from Contraceptive Use

One study gathered data from a variety of sources which have estimated the mortality rate associated with different methods of contraception at different ages (Table 4). These estimates include the combined risk of death associated with contraceptive methods plus the risk attributable to pregnancy in the event of method failure. Each method of contraception has its specific benefits and risks. The study concluded that with the exception of oral contraceptive users 35 and older who smoke and 40 and older who do not smoke, mortality associated with all methods of birth control is low and below that associated with childbirth.

The observation of a possible increase in risk of mortality with age for oral contraceptive users is based on data gathered in the 1970’s - but not reported until 1983.^35 However, current clinical practice involves the use of lower estrogen formulations combined with careful restriction of oral contraceptive use to women who do not have the various risk factors listed in this labeling.

Because of these changes in practice and, also, because of some limited new data which suggest that the risk of cardiovascular disease with the use of oral contraceptives may now be less than previously observed,^(100, 101) the Fertility and Maternal Health Drugs Advisory Committee was asked to review the topic in 1989. The Committee concluded that although cardiovascular disease risks may be increased with oral contraceptive use after age 40 in healthy non-smoking women (even with the newer low-dose formulations), there are also greater potential health risks associated with pregnancy in older women and with the alternative surgical and medical procedures which may be necessary if such women do not have access to effective and acceptable means of contraception.

Therefore, the Committee recommended that the benefits of low-dose oral contraceptive use by healthy non-smoking women over 40 may outweigh the possible risks. Of course, older women, as all women who take oral contraceptives, should take the lowest possible dose formulation that is effective and meets the individual patient needs.

TABLE 4: ANNUAL NUMBER OF BIRTH-RELATED OR METHOD-RELATED DEATHS ASSOCIATED WITH CONTROL OF FERTILITY PER 100,000 NON-STERILE WOMEN, BY FERTILITY CONTROL METHOD ACCORDING TO AGE.
Method of control and outcome | 15 to 19 | 20 to 24 | 25 to 29 | 30 to 34 | 35 to 39 | 40 to 44
No fertility control methods* | 7 | 7.4 | 9.1 | 14.8 | 25.7 | 28.2
Oral contraceptives non-smoker† | 0.3 | 0.5 | 0.9 | 1.9 | 13.8 | 31.6
Oral contraceptives smoker† | 2.2 | 3.4 | 6.6 | 13.5 | 51.1 | 117.2
IUD† | 0.8 | 0.8 | 1 | 1 | 1.4 | 1.4
Condom* | 1.1 | 1.6 | 0.7 | 0.2 | 0.3 | 0.4
Diaphragm/spermicide* | 1.9 | 1.2 | 1.2 | 1.3 | 2.2 | 2.8
Periodic abstinence* | 2.5 | 1.6 | 1.6 | 1.7 | 2.9 | 3.6
Adapted from H.W. Ory, ref. #35.
* Deaths are birth related
† Deaths are method related

3. MALIGNANT NEOPLASMS

Breast Cancer

Velivet is contraindicated in females who currently have or have had breast cancer because breast cancer may be hormonally sensitive [see Contraindications].

Epidemiology studies have not found a consistent association between use of combined oral contraceptives (COCs) and breast cancer risk. Studies do not show an association between ever (current or past) use of COCs and risk of breast cancer. However, some studies report a small increase in the risk of breast cancer among current or recent users (<6 months since last use) and current users with longer duration of COC use [see Postmarketing Experience].

Cervical Cancer

Some studies suggest that combination oral contraceptive use has been associated with an increase in the risk of cervical intra-epithelial neoplasia in some populations of women.45 to 48 However, there continues to be controversy about the extent to which such findings may be due to differences in sexual behavior and other factors.

In spite of many studies of the relationship between oral contraceptive use and breast and cervical cancers, a cause and-effect relationship has not been established.

4. Hepatic Neoplasia

Benign hepatic adenomas are associated with oral contraceptive use, although the incidence of benign tumors is rare in the United States. Indirect calculations have estimated the attributable risk to be in the range of 3.3 cases/100,000 for users, a risk that increases after four or more years of use especially with oral contraceptives of higher dose.^49 Rupture of rare, benign, hepatic adenomas may cause death through intra-abdominal hemorrhage.^(50, 51)

Studies from Britain have shown an increased risk of developing hepatocellular carcinoma52 to 54 in long-term (> 8 years) oral contraceptive users. However, these cancers are extremely rare in the U.S. and the attributable risk (the excess incidence) of liver cancers in oral contraceptive users approaches less than one per million users.

5. Risk of Liver Enzyme Elevations with Concomitant Hepatitis C Treatment

During clinical trials with the Hepatitis C combination drug regimen that contains ombitasvir/paritaprevir/ritonavir, with or without dasabuvir, ALT elevations greater than 5 times the upper limit of normal (ULN), including some cases greater than 20 times the ULN, were significantly more frequent in women using ethinyl estradiol-containing medications such as COCs. Discontinue Velivet (desogestrel and ethinyl estradiol tablets) prior to starting therapy with the combination drug regimen ombitasvir/paritaprevir/ritonavir, with or without dasabuvir [see CONTRAINDICATIONS]. Velivet (desogestrel and ethinyl estradiol tablets) can be restarted approximately 2 weeks following completion of treatment with the combination drug regimen.

6. Ocular Lesions

There have been clinical case reports of retinal thrombosis associated with the use of oral contraceptives. Oral contraceptives should be discontinued if there is unexplained partial or complete loss of vision; onset of proptosis or diplopia; papilledema; or retinal vascular lesions. Appropriate diagnostic and therapeutic measures should be undertaken immediately.

7. Oral Contraceptive Use Before or During Early Pregnancy

Extensive epidemiologic studies have revealed no increased risk of birth defects in women who have used oral contraceptives prior to pregnancy.55 to 57 Studies also do not suggest a teratogenic effect, particularly in so far as cardiac anomalies and limb reduction defects are concerned,^(55, 56, 58, 59) when oral contraceptives are taken inadvertently during early pregnancy.

The administration of oral contraceptives to induce withdrawal bleeding should not be used as a test for pregnancy. Oral contraceptives should not be used during pregnancy to treat threatened or habitual abortion. It is recommended that for any patient who has missed two consecutive periods, pregnancy should be ruled out. If the patient has not adhered to the prescribed schedule, the possibility of pregnancy should be considered at the first missed period. Oral contraceptive use should be discontinued if pregnancy is confirmed.

8. Gallbladder Disease

Earlier studies have reported an increased lifetime relative risk of gallbladder surgery in users of oral contraceptives and estrogens.^(60, 61) More recent studies, however, have shown that the relative risk of developing gallbladder disease among oral contraceptive users may be minimal.62 to 64 The recent findings of minimal risk may be related to the use of oral contraceptive formulations containing lower hormonal doses of estrogens and progestogens.

9. Carbohydrate and Lipid Metabolic Effects

Oral contraceptives have been shown to cause a decrease in glucose tolerance in a significant percentage of users.^17 Oral contraceptives containing greater than 75 micrograms of estrogens cause hyperinsulinism, while lower doses of estrogen cause less glucose intolerance.^65 Progestogens increase insulin secretion and create insulin resistance, this effect varying with different progestational agents.^(17, 66) However, in the non-diabetic woman, oral contraceptives appear to have no effect on fasting blood glucose.^67 Because of these demonstrated effects, prediabetic and diabetic women should be carefully monitored while taking oral contraceptives.

A small proportion of women will have persistent hypertriglyceridemia while on the pill. As discussed earlier (see WARNINGS 1.a. and 1.d.), changes in serum triglycerides and lipoprotein levels have been reported in oral contraceptive users.

10. Elevated Blood Pressure

Women with severe hypertension should not be started on hormonal contraceptives. An increase in blood pressure has been reported in women taking oral contraceptives^68 and this increase is more likely in older oral contraceptive users^69 and with continued use.^61 Data from the Royal College of General Practitioners^12 and subsequent randomized trials have shown that the incidence of hypertension increases with increasing quantities of progestogens.

Women with a history of hypertension or hypertension-related diseases, or renal disease^70 should be encouraged to use another method of contraception. If women elect to use oral contraceptives, they should be monitored closely and if significant elevation of blood pressure occurs, oral contraceptives should be discontinued. For most women, elevated blood pressure will return to normal after stopping oral contraceptives, ^69 and there is no difference in the occurrence of hypertension between ever- and never-users.^(68, 70, 71)

11. Headache

The onset or exacerbation of migraine or development of headache with a new pattern which is recurrent, persistent, or severe requires discontinuation of oral contraceptives and evaluation of the cause.

12. Bleeding Irregularities

Breakthrough bleeding and spotting are sometimes encountered in patients on oral contraceptives, especially during the first three months of use. If bleeding persists or recurs, non-hormonal causes should be considered and adequate diagnostic measures taken to rule out malignancy or pregnancy, as in the case of any abnormal vaginal bleeding. If pathology has been excluded, time or a change to another formulation may solve the problem. In the event of amenorrhea, pregnancy should be ruled out.

Some women may encounter post-pill amenorrhea or oligomenorrhea, especially when such a condition was pre-existent.

13. Ectopic Pregnancy

Ectopic as well as intrauterine pregnancy may occur in contraceptive failures.

PRECAUTIONS

1. Sexually Transmitted Diseases

Patients should be counseled that this product does not protect against HIV infection (AIDS) and other sexually transmitted diseases.

2. Physical Examination and Follow Up

It is good medical practice for all women to have annual history and physical examinations, including women using oral contraceptives. The physical examination, however, may be deferred until after initiation of oral contraceptives if requested by the woman and judged appropriate by the clinician. The physical examination should include special reference to blood pressure, breasts, abdomen and pelvic organs, including cervical cytology, and relevant laboratory tests. In case of undiagnosed, persistent or recurrent abnormal vaginal bleeding, appropriate measures should be conducted to rule out malignancy. Women with a strong family history of breast cancer or who have breast nodules should be monitored with particular care.

3. Lipid Disorders

Women who are being treated for hyperlipidemias should be followed closely if they elect to use oral contraceptives. Some progestogens may elevate LDL levels and may render the control of hyperlipidemias more difficult.

In patients with familial defects of lipoprotein metabolism receiving estrogen-containing preparations, there have been case reports of significant elevations of plasma triglycerides leading to pancreatitis.

4. Liver Function

If jaundice develops in any woman receiving oral contraceptives, the medication should be discontinued. The hormones in Velivet may be poorly metabolized in patients with impaired liver function.

5. Fluid Retention

Oral contraceptives may cause some degree of fluid retention. They should be prescribed with caution, and only with careful monitoring, in patients with conditions which might be aggravated by fluid retention.

6. Emotional Disorders

Patients becoming significantly depressed while taking oral contraceptives should stop the medication and use an alternate method of contraception in an attempt to determine whether the symptom is drug related. Women with a history of depression should be carefully observed and the drug discontinued if depression recurs to a serious degree.

7. Contact Lenses

Contact lens wearers who develop visual changes or changes in lens tolerance should be assessed by an ophthalmologist.

8. Drug Interactions

Changes in contraceptive effectiveness associated with coadministration of other drugs:

a. Anti-infective agents and anticonvulsants

Contraceptive effectiveness may be reduced when hormonal contraceptives are coadministered with some antibiotics, anticonvulsants, and other drugs that increase metabolism of contraceptive steroids. This could result in unintended pregnancy or breakthrough bleeding. Examples include barbiturates, rifampin, phenylbutazone, phenytoin, carbamazepine, felbamate, oxcarbazepine, topiramate, and griseofulvin.

Since desogestrel is mainly metabolized by the cytochrome P450 2C9 enzyme (CYP 2C9) to form etonogestrel, the active progestin, there is a possibility of interaction with CYP 2C9 substrates or inhibitors (such as: ibuprofen, piroxicam, naproxen, phenytoin, fluconazole, diclofenac, tolbutamide, glipizide, celecoxib, sulfamethoxazole, isoniazid, torsemide, irbesartan, losartan, and valsartan). The clinical relevance of these interactions is unknown.

b. Anti-HIV protease inhibitors

Several of the anti-HIV protease inhibitors have been studied with coadministration of oral combination hormonal contraceptives; significant changes (increase and decrease) in the plasma levels of the estrogen and progestin have been noted in some cases. The efficacy and safety of these oral contraceptive products may be affected with coadministration of anti-HIV protease inhibitors. Healthcare providers should refer to the label of the individual anti-HIV protease inhibitors for further drug-drug interaction information.

Concomitant Use with HCV Combination Therapy – Liver Enzyme Elevation

Do not co-administer Velivet (desogestrel and ethinyl estradiol tablets) with HCV drug combinations containing ombitasvir/paritaprevir/ritonavir, with or without dasabuvir, due to potential for ALT elevations (see WARNINGS, Risk of Liver Enzyme Elevations with Concomitant Hepatitis C Treatment).

c. Herbal products

Herbal products containing St. John’s Wort (hypericum perforatum) may induce hepatic enzymes (cytochrome P450) and p-glycoprotein transporter and may reduce the effectiveness of contraceptive steroids. This may also result in breakthrough bleeding.

Increase in plasma hormone levels associated with coadministered drugs:

Coadministration of atorvastatin and certain ethinyl estradiol containing oral contraceptives increased AUC values for ethinyl estradiol by approximately 20%. Ascorbic acid and acetaminophen may increase plasma ethinyl estradiol levels, possibly by inhibition of conjugation. CYP 3A4 inhibitors such as itraconazole or ketoconazole may increase plasma hormone levels.

Changes in plasma levels of coadministered drugs:

Combination hormonal contraceptives containing some synthetic estrogens (e.g., ethinyl estradiol) may inhibit the metabolism of other compounds. Increased plasma concentrations of cyclosporine, prednisolone, and theophylline have been reported with concomitant administration of oral contraceptives. Decreased plasma concentrations of acetaminophen and increased clearance of temazepam, salicylic acid, morphine, and clofibric acid have been noted when these drugs were administered with oral contraceptives.

No formal drug-drug interaction studies were conducted with Velivet.

9. Interactions with Laboratory Tests

Certain endocrine and liver function tests and blood components may be affected by oral contraceptives:

1. Increased prothrombin and factors VII, VIII, IX and X; decreased antithrombin 3; increased norepinephrine-induced platelet aggregability.
2. Increased thyroid binding globulin (TBG) leading to increased circulating total thyroid hormone, as measured by protein-bound iodine (PBI), T4 by column or by radioimmunoassay. Free T3 resin uptake is decreased, reflecting the elevated TBG; free T4 concentration is unaltered.
3. Other binding proteins may be elevated in serum.
4. Sex hormone-binding globulins are increased and result in elevated levels of total circulating sex steroids; however, free or biologically active levels either decrease or remain unchanged.
5. Triglycerides may be increased, and levels of various other lipids and lipoproteins may be affected.
6. Glucose tolerance may be decreased.
7. Serum folate levels may be depressed by oral contraceptive therapy. This may be of clinical significance if a woman becomes pregnant shortly after discontinuing oral contraceptives.

10. Carcinogenesis

See WARNINGS section.

11. Pregnancy

See CONTRAINDICATIONS and WARNINGS sections.

12. Nursing Mothers

Small amounts of oral contraceptive steroids have been identified in the milk of nursing mothers and a few adverse effects on the child have been reported, including jaundice and breast enlargement. In addition, combination oral contraceptives given in the postpartum period may interfere with lactation by decreasing the quantity and quality of breast milk. If possible, the nursing mother should be advised not to use oral contraceptives but to use other forms of contraception until she has completely weaned her child.

13. Pediatric Use

Safety and efficacy of Velivet tablets have been established in women of reproductive age. Safety and efficacy are expected to be the same for postpubertal adolescents under the age of 16 and for users 16 years and older. Use of this product before menarche is not indicated.

14. Geriatric Use

This product has not been studied in women over 65 years of age and is not indicated in this population.

INFORMATION FOR THE PATIENT

See Patient Labeling printed below.

ADVERSE REACTIONS

Post Marketing Experience

Five studies that compared breast cancer risk between ever-users (current or past use) of COCs and never-users of COCs reported no association between ever use of COCs and breast cancer risk, with effect estimates ranging from 0.90 to 1.12 (Figure 1).

Three studies compared breast cancer risk between current or recent COC users (<6 months since last use) and never users of COCs (Figure 1). One of these studies reported no association between breast cancer risk and COC use. The other two studies found an increased relative risk of 1.19 to 1.33 with current or recent use. Both of these studies found an increased risk of breast cancer with current use of longer duration, with relative risks ranging from 1.03 with less than one year of COC use to approximately 1.4 with more than 8 to 10 years of COC use.

Figure 1

RR = relative risk; OR = odds ratio; HR = hazard ratio. “ever COC” are females with current or past COC use; “never COC use” are females that never used COCs.

An increased risk of the following serious adverse reactions has been associated with the use of oral contraceptives (see WARNINGS section):

- Thrombophlebitis and venous thrombosis with or without embolism
- Arterial thromboembolism
- Pulmonary embolism
- Myocardial infarction
- Cerebral hemorrhage
- Cerebral thrombosis
- Hypertension
- Gallbladder disease
- Hepatic adenomas or benign liver tumors

There is evidence of an association between the following conditions and the use of oral contraceptives:

- Mesenteric thrombosis
- Retinal thrombosis

The following adverse reactions have been reported in patients receiving oral contraceptives and are believed to be drug-related:

- Nausea
- Vomiting
- Gastrointestinal symptoms (such as abdominal pain, cramps and bloating)
- Breakthrough bleeding
- Spotting
- Change in menstrual flow
- Amenorrhea
- Temporary infertility after discontinuation of treatment
- Edema/fluid retention
- Melasma/chloasma which may persist
- Breast changes: tenderness, pain, enlargement, and secretion
- Decrease in serum folate levels
- Exacerbation of porphyria
- Aggravation of varicose veins
- Change in weight or appetite (increase or decrease)
- Change in cervical ectropion and secretion
- Possible diminution in lactation when given immediately postpartum
- Cholestatic jaundice
- Migraine headache
- Rash (allergic)
- Mood changes, including depression
- Vaginitis, including candidiasis
- Change in corneal curvature (steepening)
- Intolerance to contact lenses
- Exacerbation of systemic lupus erythematosus
- Exacerbation of chorea
- Anaphylactic/anaphylactoid reactions, including urticaria, angioedema, and severe reactions with respiratory and circulatory symptoms

The following adverse reactions have been reported in users of oral contraceptives and the association has been neither confirmed nor refuted:

- Pre-menstrual syndrome
- Cataracts
- Cystitis-like syndrome
- Headache
- Nervousness
- Dizziness
- Hirsutism
- Loss of scalp hair
- Erythema multiforme
- Dysmenorrhea
- Pancreatitis
- Erythema nodosum
- Hemorrhagic eruption
- Impaired renal function
- Hemolytic uremic syndrome
- Acne
- Changes in libido
- Colitis
- Budd-Chiari Syndrome
- Optic neuritis, which may lead to partial or complete loss of vision

OVERDOSAGE

Serious ill effects have not been reported following acute ingestion of large doses of oral contraceptives by young children. Overdosage may cause nausea, and withdrawal bleeding may occur in females.

NON-CONTRACEPTIVE HEALTH BENEFITS

The following non-contraceptive health benefits related to the use of oral contraceptives are supported by epidemiologic studies which largely utilized oral contraceptive formulations containing estrogen doses exceeding 0.035 mg of ethinyl estradiol or 0.05 mg of mestranol.73 to 78

Effects on menses:

- increased menstrual cycle regularity
- decreased blood loss and decreased incidence of iron deficiency anemia
- decreased incidence of dysmenorrhea

Effects related to inhibition of ovulation:

- decreased incidence of functional ovarian cysts
- decreased incidence of ectopic pregnancies

Effects from long-term use:

- decreased incidence of fibroadenomas and fibrocystic disease of the breast
- decreased incidence of acute pelvic inflammatory disease
- decreased incidence of endometrial cancer
- decreased incidence of ovarian cancer

DOSAGE AND ADMINISTRATION

To achieve maximum contraceptive effectiveness, Velivet tablets must be taken exactly as directed, at the same time every day, and at intervals not exceeding 24 hours. Velivet tablets may be initiated using either a Sunday start or a Day 1 start.

NOTE: Seven different "day label strips" are provided to accommodate the selected start regimen. The patient should place the self-adhesive "day label strip" that corresponds to her starting day on the blister card above the first row of tablets.

During the First Cycle of Use

IMPORTANT: The possibility of ovulation and conception prior to initiation of use of Velivet tablets should be considered. A woman can begin to take Velivet tablets either on the first Sunday after the onset of her menstrual period (Sunday Start) or on the first day of her menstrual period (Day 1 Start). When switching from another oral contraceptive, Velivet tablets should be started on the same day that a new pack of the previous oral contraceptive would have been started.

Sunday Start

When initiating a Sunday start regimen, another method of contraception, such as condoms or spermicide, should be used for the first 7 consecutive days of taking Velivet tablets.

Using a Sunday start, tablets are taken daily without interruption as follows: The first beige tablet should be taken on the first Sunday after menstruation begins (if menstruation begins on Sunday, the first beige tablet is taken on that day). Tablets are then taken sequentially following the arrows marked on the dispenser. One beige tablet is taken daily for 7 days, followed by 1 orange tablet daily for 7 days, 1 pink tablet daily for 7 days, and then 1 white (inactive) tablet daily for 7 days. For all subsequent cycles, the patient then begins a new 28 tablet regimen on the next day (Sunday) after taking the last white (inactive) tablet. [If switching from a Sunday Start oral contraceptive, the first Velivet tablet should be taken on the second Sunday after the last tablet of a 21 day oral contraceptive regimen or should be taken on the first Sunday after the last inactive tablet of a 28 day regimen.]

If a patient misses 1 active tablet in Weeks 1, 2, or 3, she should take the missed tablet as soon as she remembers. If the patient misses 2 consecutive active tablets in Week 1 or Week 2, the patient should take 2 tablets the day she remembers and 2 tablets the next day; thereafter, the patient should resume taking 1 tablet daily until she finishes the cycle pack. The patient should be instructed to use a back-up method of birth control (such as condoms or spermicide) if she has intercourse in the 7 days after she restarts her pills. If the patient misses 2 consecutive pink (active) tablets in the third week or misses 3 or more active tablets in a row at any time during the cycle, the patient should keep taking 1 active tablet daily until the next Sunday. On Sunday the patient should throw out the rest of that cycle pack and start a new cycle pack that same day. The patient should be instructed to use a back-up method of birth control if she has intercourse in the 7 days after restarting her pills.

Complete instructions to facilitate patient counseling on proper pill usage can be found in Detailed Patient Labeling ("HOW TO TAKE THE PILL" section).

Day 1 Start

Counting the first day of menstruation as "Day 1", the first beige tablet should be taken on the first day of menstrual bleeding. Tablets are then taken sequentially without interruption as follows: One beige tablet daily for 7 days, then 1 orange tablet daily for 7 days, followed by 1 pink tablet daily for 7 days and then 1 white (inactive) tablet daily for 7 days. For all subsequent cycles, the patient then begins a new 28 tablet regimen on the next day after taking the last white (inactive) tablet. [If switching directly from another oral contraceptive, the first beige tablet should be taken on the same day that a new pack of the previous oral contraceptive would have been started.]

If a patient misses 1 active tablet in Weeks 1, 2, or 3, she should take the missed tablet as soon as she remembers. If the patient misses 2 consecutive active tablets in Week 1 or Week 2, the patient should take 2 tablets the day she remembers and 2 tablets the next day; thereafter, the patient should resume taking 1 tablet daily until she finishes the cycle pack. The patient should be instructed to use a back-up method of birth control (such as condoms or spermicide) if she has intercourse in the 7 days after she restarts her pills. If the patient misses 2 consecutive pink tablets in the third week or misses 3 or more active tablets in a row at any time during the cycle, the patient should throw out the rest of that cycle pack and start a new cycle pack that same day. The patient should be instructed to use a back-up method of birth control if she has intercourse in the 7 days after restarting her pills.

Complete instructions to facilitate patient counseling on proper pill usage can be found in Detailed Patient Labeling ("HOW TO TAKE THE PILL" section).

ADDITIONAL INSTRUCTIONS FOR BOTH SUNDAY AND DAY 1 STARTS

If Spotting or Breakthrough Bleeding Occurs

Breakthrough bleeding, spotting, and amenorrhea are frequent reasons for patients discontinuing oral contraceptives. In breakthrough bleeding, as in all cases of irregular bleeding from the vagina, non-functional causes should be considered. In undiagnosed persistent or recurrent abnormal bleeding from the vagina, adequate diagnostic measures are indicated to rule out pregnancy or malignancy. If both pregnancy and pathology have been excluded, time or a change to another preparation may solve the problem. Changing to an oral contraceptive with a higher estrogen content, while potentially useful in minimizing menstrual irregularity, should be done only if necessary since this may increase the risk of thromboembolic disease.

Use of Velivet in The Event of a Missed Menstrual Period

1. If the patient has not adhered to the prescribed schedule, the possibility of pregnancy should be considered at the time of the first missed period and oral contraceptive use should be discontinued if pregnancy is confirmed.

2. If the patient has adhered to the prescribed regimen and misses two consecutive periods, pregnancy should be ruled out. Oral contraceptive use should be discontinued if pregnancy is confirmed.

Use of Velivet Postpartum

The use of Velivet for contraception may be initiated 4 to 6 weeks postpartum in women who elect not to breastfeed. When the tablets are administered during the postpartum period, the increased risk of thromboembolic disease associated with the postpartum period must be considered (see CONTRAINDICATIONS and WARNINGS concerning thromboembolic disease. See also PRECAUTIONS, Nursing Mothers).

If the patient starts on Velivet postpartum, and has not yet had a period, she should be instructed to use another method of contraception until a beige tablet has been taken daily for 7 consecutive days.

HOW SUPPLIED

Velivet ® (desogestrel and ethinyl estradiol tablets USP - triphasic regimen) is available in a 28 day blister card tablet dispenser. Each 28 day treatment cycle pack consists of four different dosing phases, as follows: 7 beige, round, film-coated, biconvex, unscored tablets (debossed with stylized b on one side and 333 on the other side) containing 0.1 mg desogestrel and 0.025 mg ethinyl estradiol, USP; 7 orange, round, film-coated, biconvex, unscored tablets (debossed with stylized b on one side and 332 on the other side) containing 0.125 mg desogestrel and 0.025 mg ethinyl estradiol, USP; 7 pink, round, film-coated, biconvex, unscored tablets (debossed with stylized b on one side and 335 on the other side) containing 0.15 mg desogestrel and 0.025 mg ethinyl estradiol, USP and seven white, round, biconvex, unscored tablets (debossed with stylized b on one side and 334 on the other side) containing inert ingredients.

Boxes of 3 NDC 0555-9051-67

Storage

Store at 20° to 25°C (68° to 77°F) [See USP Controlled Room Temperature].

KEEP THIS AND ALL MEDICATIONS OUT OF THE REACH OF CHILDREN.

REFERENCES

1. Hatcher RA, Trussell J, Stewart F et al. Contraceptive Technology: Seventeenth Revised Edition, New York: Irvington Publishers, 1998, in press. 2. Stadel BV. Oral contraceptives and cardiovascular disease. (Pt. 1). N Engl J Med 1981; 305:612–618. 3. Stadel BV. Oral contraceptives and cardiovascular disease. (Pt. 2). N Engl J Med 1981; 305:672–677. 4. Adam SA, Thorogood M. Oral contraception and myocardial infarction revisited: the effects of new preparations and prescribing patterns. Br J Obstet and Gynecol 1981; 88:838–845. 5. Mann JI, Inman WH. Oral contraceptives and death from myocardial infarction. Br Med J 1975; 2(5965):245–248. 6. Mann JI, Vessey MP, Thorogood M, Doll R. Myocardial infarction in young women with special reference to oral contraceptive practice. Br Med J 1975; 2(5956):241–245. 7. Royal College of General Practitioners’ Oral Contraception Study: Further analyses of mortality in oral contraceptive users. Lancet 1981; 1:541–546. 8. Slone D, Shapiro S, Kaufman DW, Rosenberg L, Miettinen OS, Stolley PD. Risk of myocardial infarction in relation to current and discontinued use of oral contraceptives. N Engl J Med 1981; 305:420–424. 9. Vessey MP. Female hormones and vascular disease—an epidemiological overview. Br J Fam Plann 1980; 6:1–12. 10. Russell-Briefel RG, Ezzati TM, Fulwood R, Perlman JA, Murphy RS. Cardiovascular risk status and oral contraceptive use, United States, 1976–80. Prevent Med 1986; 15:352–362. 11. Goldbaum GM, Kendrick JS, Hogelin GC, Gentry EM. The relative impact of smoking and oral contraceptive use on women in the United States. JAMA 1987; 258:1339–1342. 12. Layde PM, Beral V. Further analyses of mortality in oral contraceptive users: Royal College General Practitioners’ Oral Contraception Study. (Table 5) Lancet 1981; 1:541–546. 13. Knopp RH. Arteriosclerosis risk: the roles of oral contraceptives and postmenopausal estrogens. J Reprod Med 1986; 31(9) (Supplement):913–921. 14. Krauss RM, Roy S, Mishell DR, Casagrande J, Pike MC. Effects of two low-dose oral contraceptives on serum lipids and lipoproteins: Differential changes in high-density lipoproteins subclasses. Am J Obstet 1983; 145:446–452. 15. Wahl P, Walden C, Knopp R, Hoover J, Wallace R, Heiss G, Rifkind B. Effect of estrogen/progestin potency on lipid/lipoprotein cholesterol. N Engl J Med 1983; 308:862–867. 16. Wynn V, Niththyananthan R. The effect of progestin in combined oral contraceptives on serum lipids with special reference to high-density lipoproteins. Am J Obstet Gynecol 1982; 142:766–771. 17. Wynn V, Godsland I. Effects of oral contraceptives and carbohydrate metabolism. J Reprod Med 1986; 31 (9) (Supplement):892–897. 18. LaRosa JC. Atherosclerotic risk factors in cardiovascular disease. J Reprod Med 1986; 31 (9) (Supplement):906–912. 19. Inman WH, Vessey MP. Investigation of death from pulmonary, coronary, and cerebral thrombosis and embolism in women of child-bearing age. Br Med J 1968; 2 (5599):193–199. 20. Maguire MG, Tonascia J, Sartwell PE, Stolley PD, Tockman MS. Increased risk of thrombosis due to oral contraceptives: a further report. Am J Epidemiol 1979; 110 (2):188–195. 21. Pettiti DB, Wingerd J, Pellegrin F, Ramacharan S. Risk of vascular disease in women: smoking, oral contraceptives, noncontraceptive estrogens, and other factors. JAMA 1979; 242:1150–1154. 22. Vessey MP, Doll R. Investigation of relation between use of oral contraceptives and thromboembolic disease. Br Med J 1968; 2 (5599):199–205. 23. Vessey MP, Doll R. Investigation of relation between use of oral contraceptives and thromboembolic disease. A further report. Br Med J 1969; 2 (5658):651–657. 24. Porter JB, Hunter JR, Danielson DA, Jick H, Stergachis A. Oral contraceptives and non-fatal vascular disease—recent experience. Obstet Gynecol 1982; 59 (3):299–302. 25. Vessey M, Doll R, Peto R, Johnson B, Wiggins P. A long-term follow-up study of women using different methods of contraception: an interim report. Biosocial Sci 1976; 8:375–427. 26. Royal College of General Practitioners: Oral contraceptives, venous thrombosis, and varicose veins. J Royal Coll Gen Pract 1978; 28:393–399. 27. Collaborative Group for the Study of Stroke in Young Women: Oral contraception and increased risk of cerebral ischemia or thrombosis. N Engl J Med 1973; 288:871–878. 28. Petitti DB, Wingerd J. Use of oral contraceptives, cigarette smoking, and risk of subarachnoid hemorrhage. Lancet 1978; 2:234–236. 29. Inman WH. Oral contraceptives and fatal subarachnoid hemorrhage. Br Med J 1979; 2 (6203):1468–70. 30. Collaborative Group for the Study of Stroke in Young Women: Oral contraceptives and stroke in young women: associated risk factors. JAMA 1975; 231:718–722. 31. Inman WH, Vessey MP, Westerholm B, Engelund A. Thromboembolic disease and the steroidal content of oral contraceptives. A report to the Committee on Safety of Drugs. Br Med J 1970; 2:203–209. 32. Meade TW, Greenberg G, Thompson SG. Progestogens and cardiovascular reactions associated with oral contraceptives and a comparison of the safety of 50- and 35-mcg oestrogen preparations. Br Med J 1980; 280 (6224):1157–1161. 33. Kay CR. Progestogens and arterial disease—evidence from the Royal College of General Practitioners’ Study. Am J Obstet Gynecol 1982; 142:762–765. 34. Royal College of General Practitioners: Incidence of arterial disease among oral contraceptive users. J Royal Coll Gen Pract 1983; 33:75–82. 35. Ory HW. Mortality associated with fertility and fertility control: 1983. Family Planning Perspectives 1983; 15:50–56. 36. The Cancer and Steroid Hormone Study of the Centers for Disease Control and the National Institute of Child Health and Human Development: Oral-contraceptive use and the risk of breast cancer. N Engl J Med 1986; 315:405–411. 37. Pike MC, Henderson BE, Krailo MD, Duke A, Roy S. Breast cancer risk in young women and use of oral contraceptives: possible modifying effect of formulation and age at use. Lancet 1983; 2:926–929. 38. Paul C, Skegg DG, Spears GFS, Kaldor JM. Oral contraceptives and breast cancer: A national study. Br Med J 1986; 293:723–725. 39. Miller DR, Rosenberg L, Kaufman DW, Schottenfeld D, Stolley PD, Shapiro S. Breast cancer risk in relation to early oral contraceptive use. Obstet Gynecol 1986; 68:863–868. 40. Olson H, Olson KL, Moller TR, Ranstam J, Holm P. Oral contraceptive use and breast cancer in young women in Sweden (letter). Lancet 1985; 2:748–749. 41. McPherson K, Vessey M, Neil A, Doll R, Jones L, Roberts M. Early contraceptive use and breast cancer: Results of another case-control study. Br J Cancer 1987; 56:653–660. 42. Huggins GR, Zucker PF. Oral contraceptives and neoplasia: 1987 update. Fertil Steril 1987; 47:733–761. 43. McPherson K, Drife JO. The pill and breast cancer: why the uncertainty? Br Med J 1986; 293:709–710. 44. Shapiro S. Oral contraceptives—time to take stock. N Engl J Med 1987; 315:450–451. 45. Ory H, Naib Z, Conger SB, Hatcher RA, Tyler CW. Contraceptive choice and prevalence of cervical dysplasia and carcinoma in situ. Am J Obstet Gynecol 1976; 124:573–577. 46. Vessey MP, Lawless M, McPherson K, Yeates D. Neoplasia of the cervix uteri and contraception: a possible adverse effect of the pill. Lancet 1983; 2:930. 47. Brinton LA, Huggins GR, Lehman HF, Malli K, Savitz DA, Trapido E, Rosenthal J, Hoover R. Long-term use of oral contraceptives and risk of invasive cervical cancer. Int J Cancer 1986; 38:339–344. 48. WHO Collaborative Study of Neoplasia and Steroid Contraceptives: Invasive cervical cancer and combined oral contraceptives. Br Med J 1985; 209:961–965. 49. Rooks JB, Ory HW, Ishak KG, Strauss LT, Greenspan JR, Hill AP, Tyler CW. Epidemiology of hepatocellular adenoma: the role of oral contraceptive use. JAMA 1979; 242:644–648. 50. Bein NN, Goldsmith HS. Recurrent massive hemorrhage from benign hepatic tumors secondary to oral contraceptives. Br J Surg 1977; 64:433–435. 51. Klatskin G. Hepatic tumors: possible relationship to use of oral contraceptives. Gastroenterology 1977; 73:386–394. 52. Henderson BE, Preston-Martin S, Edmondson HA, Peters RL, Pike MC. Hepatocellular carcinoma and oral contraceptives. Br J Cancer 1983; 48:437–440. 53. Neuberger J, Forman D, Doll R, Williams R. Oral contraceptives and hepatocellular carcinoma. Br Med J 1986; 292:1355–1357. 54. Forman D, Vincent TJ, Doll R. Cancer of the liver and oral contraceptives. Br Med J 1986; 292:1357–1361. 55. Harlap S, Eldor J. Births following oral contraceptive failures. Obstet Gynecol 1980; 55:447–452. 56. Savolainen E, Saksela E, Saxen L. Teratogenic hazards of oral contraceptives analyzed in a national malformation register. Am J Obstet Gynecol 1981; 140:521–524. 57. Janerich DT, Piper JM, Glebatis DM. Oral contraceptives and birth defects. Am J Epidemiol 1980; 112:73–79. 58. Ferencz C, Matanoski GM, Wilson PD, Rubin JD, Neill CA, Gutberlet R. Maternal hormone therapy and congenital heart disease. Teratology 1980; 21:225–239. 59. Rothman KJ, Fyler DC, Goldblatt A, Kreidberg MB. Exogenous hormones and other drug exposures of children with congenital heart disease. Am J Epidemiol 1979; 109:433–439. 60. Boston Collaborative Drug Surveillance Program: Oral contraceptives and venous thromboembolic disease, surgically confirmed gallbladder disease, and breast tumors. Lancet 1973; 1:1399–1404. 61. Royal College of General Practitioners: Oral contraceptives and health. New York, Pittman, 1974. 62. Layde PM, Vessey MP, Yeates D. Risk of gallbladder disease: a cohort study of young women attending family planning clinics. J Epidemiol Community Health 1982; 36:274–278. 63. Rome Group for the Epidemiology and Prevention of Cholelithiasis (GREPCO): Prevalence of gallstone disease in an Italian adult female population. Am J Epidemiol 1984; 119:796–805. 64. Strom BL, Tamragouri RT, Morse ML, Lazar EL, West SL, Stolley PD, Jones JK. Oral contraceptives and other risk factors for gallbladder disease. Clin Pharmacol Ther 1986; 39:335–341. 65. Wynn V, Adams PW, Godsland IF, Melrose J, Niththyananthan R, Oakley NW, Seedj A. Comparison of effects of different combined oral-contraceptive formulations on carbohydrate and lipid metabolism. Lancet 1979; 1:1045–1049. 66. Wynn V. Effect of progesterone and progestins on carbohydrate metabolism. In Progesterone and Progestin. Edited by Bardin CW, Milgrom E, Mauvis-Jarvis P. New York, Raven Press, 1983 pp. 395–410. 67. Perlman JA, Roussell-Briefel RG, Ezzati TM, Lieberknecht G. Oral glucose tolerance and the potency of oral contraceptive progestogens. J Chronic Dis 1985; 38:857–864. 68. Royal College of General Practitioners’ Oral Contraception Study: Effect on hypertension and benign breast disease of progestogen component in combined oral contraceptives. Lancet 1977; 1:624. 69. Fisch IR, Frank J. Oral contraceptives and blood pressure. JAMA 1977; 237:2499–2503. 70. Laragh AJ. Oral contraceptive induced hypertension—nine years later. Am J Obstet Gynecol 1976; 126:141–147. 71. Ramcharan S, Peritz E, Pellegrin FA, Williams WT. Incidence of hypertension in the Walnut Creek Contraceptive Drug Study cohort. In Pharmacology of Steroid Contraceptive Drugs. Garattini S, Berendes HW. Eds. New York, Raven Press, 1977 pp. 277–288. (Monographs of the Mario Negri Institute for Pharmacological Research, Milan). 72. Stockley I. Interactions with oral contraceptives. J Pharm 1976; 216:140–143. 73. The Cancer and Steroid Hormone Study of the Centers for Disease Control and the National Institute of Child Health and Human Development: Oral contraceptive use and the risk of ovarian cancer. JAMA 1983; 249:1596–1599. 74. The Cancer and Steroid Hormone Study of the Centers for Disease Control and the National Institute of Child Health and Human Development: Combination oral contraceptive use and the risk of endometrial cancer. JAMA 1987; 257:796–800. 75. Ory HW. Functional ovarian cysts and oral contraceptives: negative association confirmed surgically. JAMA 1974; 228:68–69. 76. Ory HW, Cole P, Macmahon B, Hoover R. Oral contraceptives and reduced risk of benign breast disease. N Engl J Med 1976; 294:419–422. 77. Ory HW. The noncontraceptive health benefits from oral contraceptive use. Fam Plann Perspect 1982; 14:182–184. 78. Ory HW, Forrest JD, Lincoln R. Making Choices: Evaluating the health risks and benefits of birth control methods. New York, The Alan Guttmacher Institute, 1983; p. 1. 79. Schlesselman J, Stadel BV, Murray P, Lai S. Breast Cancer in relation to early use of oral contraceptives 1988; 259:1828–1833. 80. Hennekens CH, Speizer FE, Lipnick RJ, Rosner B, Bain C, Belanger C, Stampfer MJ, Willett W, Peto R. A case-controlled study of oral contraceptive use and breast cancer. JNCI 1984; 72:39–42. 81. LaVecchia C, Decarli A, Fasoli M, Franceschi S, Gentile A, Negri E, Parazzini F, Tognoni G. Oral contraceptives and cancers of the breast and of the female genital tract. Interim results from a case-control study. Br. J. Cancer 1986; 54:311–317. 82. Meirik O, Lund E, Adami H, Bergstrom R, Christoffersen T, Bergsjo P. Oral contraceptive use in breast cancer in young women. A Joint National Case-control study in Sweden and Norway. Lancet 1986; 11:650–654. 83. Kay CR, Hannaford PC. Breast cancer and the pill—A further report from the Royal College of General Practitioners’ oral contraception study. Br. J. Cancer 1988; 58:675–680. 84. Stadel BV, Lai S, Schlesselman JJ, Murray P. Oral contraceptives and premenopausal breast cancer in nulliparous women. Contraception 1988; 38:287–299. 85. Miller DR, Rosenberg L, Kaufman DW, Stolley P, Warshauer ME, Shapiro S. Breast cancer before age 45 and oral contraceptive use: New Findings. Am. J. Epidemiol 1989; 129:269–280. 86. The UK National Case-Control Study Group, Oral contraceptive use and breast cancer risk in young women. Lancet 1989; 1:973–982. 87. Schlesselman JJ. Cancer of the breast and reproductive tract in relation to use of oral contraceptives. Contraception 1989; 40:1–38. 88. Vessey MP, McPherson K, Villard-Mackintosh L, Yeates D. Oral contraceptives and breast cancer: latest findings in a large cohort study. Br. J. Cancer 1989; 59:613–617. 89. Jick SS, Walker AM, Stergachis A, Jick H. Oral contraceptives and breast cancer. Br. J. Cancer 1989; 59:618–621. 90. Godsland, I et al. The effects of different formulations of oral contraceptive agents on lipid and carbohydrate metabolism. N Engl J Med 1990; 323:1375–81. 91. Kloosterboer, HJ et al. Selectivity in progesterone and androgen receptor binding of progestogens used in oral contraception. Contraception, 1988; 38:325–32. 92. Van der Vies, J and de Visser, J. Endocrinological studies with desogestrel. Arzneim. Forsch./Drug Res., 1983; 33(l),2:231–6. 93. Data on file, Organon Inc. 94. Fotherby, K. Oral contraceptives, lipids and cardiovascular diseases. Contraception, 1985; Vol. 31; 4:367–94. 95. Lawrence, DM et al. Reduced sex hormone binding globulin and derived free testosterone levels in women with severe acne. Clinical Endocrinology, 1981; 15:87–91. 96. Cullberg, G et al. Effects of a low-dose desogestrel-ethinyl estradiol combination on hirsutism, androgens and sex hormone binding globulin in women with a polycystic ovary syndrome. Acta Obstet Gynecol Scand, 1985; 64:195–202. 97. Jung-Hoffmann, C and Kuhl, H. Divergent effects of two low-dose oral contraceptives on sex hormone-binding globulin and free testosterone. AJOG, 1987; 156:199–203. 98. Hammond, G et al. Serum steroid binding protein concentrations, distribution of progestogens, and bioavailability of testosterone during treatment with contraceptives containing desogestrel or levonorgestrel. Fertil. Steril., 1984; 42:44–51. 99. Palatsi, R et al. Serum total and unbound testosterone and sex hormone-binding globulin (SHBG) in female acne patients treated with two different oral contraceptives. Acta Derm Venereol, 1984; 64:517–23. 100. Porter JB, Hunter J, Jick H et al. Oral contraceptives and nonfatal vascular disease. Obstet Gynecol 1985; 66:1–4. 101. Porter JB, Jick H, Walker AM. Mortality among oral contraceptive users. Obstet Gynecol 1987; 7029–32. 102. Jick H, Jick SS, Gurewich V, Myers MW, Vasilakis C. Risk of idiopathic cardiovascular death and non-fatal venous thromboembolism in women using oral contraceptives with differing progestagen components. Lancet, 1995; 346:1589–93. 103. World Health Organization Collaborative Study of Cardiovascular Disease and Steroid Hormone Contraception. Effect of different progestagens in low oestrogen oral contraceptives on venous thromboembolic disease. Lancet, 1995; 346:1582–88. 104. Spitzer WO, Lewis MA, Heinemann LAJ, Thorogood M, MacRae KD on behalf of Transnational Research Group on Oral Contraceptives and Health of Young Women. Third generation oral contraceptives and risk of venous thromboembolic disorders: An international case-control study. Br Med J, 1996; 312:83–88.

Teva Pharmaceuticals USA, Inc.

North Wales, PA 19454

Rev. C 9/2022

DETAILED PATIENT PACKAGE INSERT

Velivet®
(desogestrel and ethinyl estradiol tablets USP - triphasic regimen)

28 Day Regimen

This product (like all oral contraceptives) is intended to prevent pregnancy. It does not protect against HIV infection (AIDS) and other sexually transmitted diseases.

PLEASE NOTE: This labeling is revised from time to time as important new medical information becomes available. Therefore, please review this labeling carefully.

DESCRIPTION

Velivet tablets are a triphasic oral contraceptive product, containing a combination of a progestin and estrogen, the two kinds of female hormones.

Each beige tablet contains 0.1 mg desogestrel and 0.025 mg ethinyl estradiol; each orange tablet contains 0.125 mg desogestrel and 0.025 mg ethinyl estradiol; and each pink tablet contains 0.15 mg desogestrel and 0.025 mg ethinyl estradiol. Each white tablet contains inert ingredients.

INTRODUCTION

Any woman who considers using oral contraceptives (the birth control pill or the pill) should understand the benefits and risks of using this form of birth control. This leaflet will give you much of the information you will need to make this decision and will also help you determine if you are at risk of developing any of the serious side effects of the pill. It will tell you how to use the pill properly so that it will be as effective as possible. However, this leaflet is not a replacement for a careful discussion between you and your doctor or healthcare provider. You should discuss the information provided in this leaflet with him or her, both when you first start taking the pill and during your revisits. You should also follow your doctor’s or healthcare provider’s advice with regard to regular check-ups while you are on the pill.

EFFECTIVENESS OF ORAL CONTRACEPTIVES

Oral contraceptives or “birth control pills” or “the pill” are used to prevent pregnancy and are more effective than other non-surgical methods of birth control. When they are taken correctly, the chance of becoming pregnant is less than 1% (1 pregnancy per 100 women per year of use), when used perfectly, without missing any pills. Typical failure rates are actually 5% (5 pregnancies per 100 women per year of use). The chance of becoming pregnant increases with each missed pill during a menstrual cycle.

In comparison, typical failure rates for other methods of birth control during the first year of use are as follows:

No methods: 85%

Spermicides alone: 26%

Periodic abstinence: 25%

Condom alone (female): 21%

Cervical Cap with spermicides: 20 to 40%

Vaginal sponge: 20 to 40%

Diaphragm with spermicides: 20%

Withdrawal: 19%

Condom alone (male): 14%

IUD: less than 1 to 2%

Implants: less than 1%

Injectable progestogen: less than 1%

Male sterilization: less than 1%

Female sterilization: less than 1%

WHO SHOULD NOT TAKE ORAL CONTRACEPTIVES

Cigarette smoking increases the risk of serious cardiovascular side effects from oral contraceptive use. This risk increases with age and with heavy smoking (15 or more cigarettes per day) and is quite marked in women over 35 years of age. Women who use oral contraceptives are strongly advised not to smoke.

Some women should not use the pill. For example, you should not take the pill if you are pregnant or think you may be pregnant. You should also not use the pill if you have any of the following conditions:

- A history of heart attack or stroke
- A history of blood clots in the legs (thrombophlebitis), lungs (pulmonary embolism), or eyes
- A history of blood clots in the deep veins of your legs
- Chest pain (angina pectoris)
- Severe high blood pressure
- Diabetes with complications of the kidneys, eyes, nerves, or blood vessels
- Headache with neurological symptoms
- Known or suspected breast cancer or cancer of the lining of the uterus, cervix, or vagina (now or in the past)
- Unexplained vaginal bleeding (until a diagnosis is reached by your healthcare provider)
- Yellowing of the whites of the eyes or of the skin (jaundice) during pregnancy or during previous use of hormonal birth control of any kind (the pill, patch, vaginal ring, injection, or implant)
- Liver tumor (benign or cancerous)
- Heart valve or heart rhythm disorders that may be associated with formation of blood clots
- Need for a long period of bed rest following major surgery
- Known or suspected pregnancy
- Active liver disease with abnormal liver function tests
- Take any Hepatitis C drug combination containing ombitasvir/paritaprevir/ritonavir, with or without dasabuvir. This may increase levels of the liver enzyme "alanine aminotransferase" (ALT) in the blood
- An allergy or hypersensitivity to any of the components of Velivet (desogestrel and ethinyl estradiol tablets)

Tell your doctor or healthcare provider if you have ever had any of the above conditions. Your doctor or healthcare provider can recommend another method of birth control.

OTHER CONSIDERATIONS BEFORE TAKING ORAL CONTRACEPTIVES

Tell your doctor or healthcare provider if you have:

- Breast nodules, fibrocystic disease of the breast, an abnormal breast x-ray or mammogram
- Diabetes
- Elevated cholesterol or triglycerides
- High blood pressure
- Migraine or other headaches or epilepsy
- Depression
- Gallbladder, liver, heart, or kidney disease
- Scanty or irregular menstrual periods

Women with any of these conditions should be checked often by their doctor or healthcare provider if they choose to use oral contraceptives.

Talk to your healthcare provider about using Velivet if you:

- Smoke
- Recently had a baby
- Recently had a miscarriage or abortion
- Are breastfeeding
- Are taking any other medications

RISKS OF TAKING ORAL CONTRACEPTIVES

1. Risk of Developing Blood Clots

Blood clots and blockage of blood vessels are one of the most serious side effects of taking oral contraceptives and can cause death or serious disability. In particular, a clot in the leg can cause thrombophlebitis and a clot that travels to the lungs can cause a sudden blockage of a vessel carrying blood to the lungs. The risks of these side effects may be greater with desogestrel-containing oral contraceptives, such as Velivet (desogestrel and ethinyl estradiol tablets) than with certain other low-dose pills. Rarely, clots occur in the blood vessels of the eye and may cause blindness, double vision, or impaired vision.

If you take oral contraceptives and need elective surgery, need to stay in bed for a prolonged illness or have recently delivered a baby, you may be at risk of developing blood clots. You should consult your doctor or healthcare provider about stopping oral contraceptives three to four weeks before surgery and not taking oral contraceptives for two weeks after surgery or during bed rest. You should also not take oral contraceptives soon after delivery of a baby. It is advisable to wait for at least four weeks after delivery if you are not breastfeeding. If you are breastfeeding, you should wait until you have weaned your child before using the pill (see GENERAL PRECAUTIONS, While Breastfeeding).

The risk of circulatory disease in oral contraceptive users may be higher in users of high-dose pills and may be greater with longer duration of oral contraceptive use. In addition, some of these increased risks may continue for a number of years after stopping oral contraceptives. The risk of venous thromboembolic disease associated with oral contraceptives does not increase with length of use and disappears after pill use is stopped. The risk of abnormal blood clotting increases with age in both users and non-users of oral contraceptives, but the increased risk from the oral contraceptive appears to be present at all ages. For women aged 20 to 44 it is estimated that about 1 in 2000 using oral contraceptives will be hospitalized each year because of abnormal clotting. Among non-users in the same age group, about 1 in 20,000 would be hospitalized each year. For oral contraceptive users in general, it has been estimated that in women between the ages of 15 and 34 the risk of death due to a circulatory disorder is about 1 in 12,000 per year, whereas for non-users the rate is about 1 in 50,000 per year. In the age group 35 to 44, the risk is estimated to be about 1 in 2500 per year for oral contraceptive users and about 1 in 10,000 per year for non-users.

2. Heart Attacks and Strokes

Oral contraceptives may increase the tendency to develop strokes (blockage or rupture of blood vessels in the brain), angina pectoris (chest pain), and heart attacks (blockage of blood vessels in the heart). Any of these conditions can cause death or serious disability.

Smoking greatly increases the possibility of suffering heart attacks and strokes. Furthermore, smoking and the use of oral contraceptives greatly increase the chances of developing and dying of heart disease.

Women with migraine (especially migraine with aura) who take oral contraceptives also may be at a higher risk of stroke.

3. Gallbladder Disease

Oral contraceptive users probably have a greater risk than non-users of having gallbladder disease, although this risk may be related to pills containing high doses of estrogens.

4. Liver Tumors

In rare cases, oral contraceptives can cause benign but dangerous liver tumors. These benign liver tumors can rupture and cause fatal internal bleeding. In addition, a possible, but not definite, association has been found with the pill and liver cancers in two studies, in which a few women who developed these very rare cancers were found to have used oral contraceptives for long periods. However, liver cancers are extremely rare. The chance of developing liver cancer from using the pill is thus even rarer.

5. Risk of Cancer

It is not known if hormonal birth control pills cause breast cancer. Some studies, but not all, suggest that there could be a slight increase in the risk of breast cancer among current users with longer duration of use.

If you have breast cancer now, or have had it in the past, do not use hormonal birth control because some breast cancers are sensitive to hormones.

Some studies have found an increase in the incidence of cancer of the cervix in women who use oral contraceptives. However, this finding may be related to factors other than the use of oral contraceptives. There is insufficient evidence to rule out the possibility that pills may cause such cancers.

6. Lipid Metabolism and Inflammation of the Pancreas

In patients with inherited defects of lipid metabolism, there have been reports of significant elevations of plasma triglycerides during estrogen therapy. This has led to pancreatitis in some cases.

ESTIMATED RISK OF DEATH FROM A BIRTH CONTROL METHOD OR PREGNANCY

All methods of birth control and pregnancy are associated with a risk of developing certain diseases which may lead to disability or death. An estimate of the number of deaths associated with different methods of birth control and pregnancy has been calculated and is shown in the following table.

ANNUAL NUMBER OF BIRTH-RELATED OR METHOD-RELATED DEATHS ASSOCIATED WITH CONTROL OF FERTILITY PER 100,000 NON-STERILE WOMEN, BY FERTILITY CONTROL METHOD ACCORDING TO AGE
Method of control and outcome | 15 to 19 | 20 to 24 | 25 to 29 | 30 to 34 | 35 to 39 | 40 to 44
No fertility control methods* | 7.0 | 7.4 | 9.1 | 14.8 | 25.7 | 28.2
Oral contraceptives non-smoker† | 0.3 | 0.5 | 0.9 | 1.9 | 13.8 | 31.6
Oral contraceptives smoker† | 2.2 | 3.4 | 6.6 | 13.5 | 51.1 | 117.2
IUD† | 0.8 | 0.8 | 1.0 | 1.0 | 1.4 | 1.4
Condom* | 1.1 | 1.6 | 0.7 | 0.2 | 0.3 | 0.4
Diaphragm/spermicide* | 1.9 | 1.2 | 1.2 | 1.3 | 2.2 | 2.8
Periodic abstinence* | 2.5 | 1.6 | 1.6 | 1.7 | 2.9 | 3.6
*Deaths are birth related
†Deaths are method related

In the above table, the risk of death from any birth control method is less than the risk of childbirth, except for oral contraceptive users over the age of 35 who smoke and pill users over the age of 40 even if they do not smoke. It can be seen in the table that for women aged 15 to 39, the risk of death was highest with pregnancy (7 to 26 deaths per 100,000 women, depending on age). Among pill users who do not smoke, the risk of death is always lower than that associated with pregnancy for any age group, although over the age of 40, the risk increases to 32 deaths per 100,000 women, compared to 28 associated with pregnancy at that age. However, for pill users who smoke and are over the age of 35, the estimated number of deaths exceeds those for other methods of birth control. If a woman is over the age of 40 and smokes, her estimated risk of death is four times higher (117 per 100,000 women) than the estimated risk associated with pregnancy (28 per 100,000 women) in that age group.

The suggestion that women over 40 who do not smoke should not take oral contraceptives is based on information from older, high-dose pills and on less selective use of pills than is practiced today. An Advisory Committee of the FDA discussed this issue in 1989 and recommended that the benefits of oral contraceptive use by healthy, non-smoking women over 40 years of age may outweigh the possible risks. However, all women, especially older women, are cautioned to use the lowest dose pill that is effective.

WARNING SIGNALS

If any of these adverse effects occur while you are taking oral contraceptives, call your doctor or healthcare provider immediately:

- Sharp chest pain, coughing of blood, or sudden shortness of breath (indicating a possible clot in the lung)
- Pain in the calf (indicating a possible clot in the leg)
- Crushing chest pain or heaviness in the chest (indicating a possible heart attack)
- Sudden severe headache or vomiting, dizziness or fainting, disturbances of vision or speech, weakness, or numbness in an arm or leg (indicating a possible stroke)
- Sudden partial or complete loss of vision (indicating a possible clot in the eye)
- Breast lumps (indicating possible breast cancer or fibrocystic disease of the breast; ask your doctor or healthcare provider to show you how to examine your breasts)
- Severe pain or tenderness in the stomach area (indicating a possibly ruptured liver tumor)
- Difficulty in sleeping, weakness, lack of energy, fatigue, or change in mood (possibly indicating severe depression)
- Jaundice or a yellowing of the skin or eyeballs, accompanied frequently by fever, fatigue, loss of appetite, dark colored urine, or light colored bowel movements (indicating possible liver problems)

SIDE EFFECTS OF ORAL CONTRACEPTIVES

In addition to the risks and more serious side effects discussed above (see RISKS OF TAKING ORAL CONTRACEPTIVES, ESTIMATED RISK OF DEATH FROM A BIRTH CONTROL METHOD OR PREGNANCY and WARNING SIGNALS sections), the following may also occur:

1. Irregular Vaginal Bleeding

Irregular vaginal bleeding or spotting may occur while you are taking the pills. Irregular bleeding may vary from slight staining between menstrual periods to breakthrough bleeding, which is a flow much like a regular period. Irregular bleeding occurs most often during the first few months of oral contraceptive use, but may also occur after you have been taking the pill for some time. Such bleeding may be temporary and usually does not indicate any serious problems. It is important to continue taking your pills on schedule. If the bleeding occurs in more than one cycle or lasts for more than a few days, talk to your doctor or healthcare provider.

2. Contact Lenses

If you wear contact lenses and notice a change in vision or an inability to wear your lenses, contact your doctor or healthcare provider.

3. Fluid Retention or Raised Blood Pressure

Oral contraceptives may cause edema (fluid retention) with swelling of the fingers or ankles and may raise your blood pressure. If you experience fluid retention, contact your doctor or healthcare provider.

4. Melasma

A spotty darkening of the skin is possible, particularly of the face.

5. Other Side Effects

Other side effects may include nausea and vomiting, change in appetite, headache, nervousness, depression, dizziness, loss of scalp hair, rash, and vaginal infections.

If any of these side effects bother you, call your doctor or healthcare provider.

GENERAL PRECAUTIONS

1. Missed Periods and Use of Oral Contraceptives Before or During Early Pregnancy

There may be times when you may not menstruate regularly after you have completed taking a cycle of pills. If you have taken your pills regularly and miss one menstrual period, continue taking your pills for the next cycle but be sure to inform your doctor or healthcare provider before doing so. If you have not taken the pills daily as instructed and missed a menstrual period, or if you missed two consecutive menstrual periods, you may be pregnant. Check with your doctor or healthcare provider immediately to determine whether you are pregnant. Stop taking Velivet (desogestrel and ethinyl estradiol tablets) if you are pregnant.

There is no conclusive evidence that oral contraceptive use is associated with an increase in birth defects, when taken inadvertently during early pregnancy. Previously, a few studies had reported that oral contraceptives might be associated with birth defects, but these studies have not been confirmed. Nevertheless, oral contraceptives or any other drugs should not be used during pregnancy unless clearly necessary and prescribed by your doctor or healthcare provider. You should check with your doctor or healthcare provider about risks to your unborn child of any medication taken during pregnancy.

2. While Breastfeeding

If you are breastfeeding, consult your doctor or healthcare provider before starting oral contraceptives. Some of the drug will be passed on to the child in the milk. A few adverse effects on the child have been reported, including yellowing of the skin (jaundice) and breast enlargement. In addition, oral contraceptives may decrease the amount and quality of your milk. If possible, do not use oral contraceptives while breastfeeding. You should use another method of contraception since breastfeeding provides only partial protection from becoming pregnant and this partial protection decreases significantly as you breastfeed for longer periods of time. You should consider starting oral contraceptives only after you have weaned your child completely.

3. Laboratory Tests

If you are scheduled for any laboratory tests, tell your doctor or healthcare provider you are taking birth control pills. Certain blood tests may be affected by birth control pills.

4. Drug Interactions

Certain drugs may interact with birth control pills to make them less effective in preventing pregnancy or cause an increase in breakthrough bleeding. Such drugs include rifampin, drugs used for epilepsy such as barbiturates (for example, phenobarbital), phenytoin (Dilantin® is one brand of this drug), phenylbutazone (Butazolidin® is one brand), herbal products containing St. John’s Wort (hypericum perforatum), and possibly certain antibiotics. You may need to use additional contraception when you take drugs which can make oral contraceptives less effective. Be sure to tell your healthcare provider if you are taking or start taking any medications while taking birth control pills.

5. Sexually Transmitted Diseases

This product (like all oral contraceptives) is intended to prevent pregnancy. It does not protect against transmission of HIV (AIDS) and other sexually transmitted diseases such as chlamydia, genital herpes, genital warts, gonorrhea, hepatitis B, and syphilis.

HOW TO TAKE VELIVET

IMPORTANT POINTS TO REMEMBER

BEFORE YOU START TAKING YOUR PILLS:

1. BE SURE TO READ THESE DIRECTIONS:

- Before you start taking your pills
- Anytime you are not sure what to do

2. THE RIGHT WAY TO TAKE THE PILL IS TO TAKE ONE PILL EVERY DAY AT THE SAME TIME. If you miss pills you could get pregnant. This includes starting the pack late. The more pills you miss, the more likely you are to get pregnant.

3. MANY WOMEN HAVE SPOTTING OR LIGHT BLEEDING, OR MAY FEEL SICK TO THEIR STOMACH DURING THE FIRST 1 TO 3 PACKS OF PILLS. If you have spotting or light bleeding or feel sick to your stomach, do not stop taking the pill. The problem will usually go away. If it doesn't go away, check with your doctor or healthcare provider.

4. MISSING PILLS CAN ALSO CAUSE SPOTTING OR LIGHT BLEEDING, even when you make up these missed pills. On the days you take 2 pills to make up for missed pills, you could also feel a little sick to your stomach.

5. IF YOU HAVE VOMITING OR DIARRHEA, for any reason, or IF YOU TAKE CERTAIN MEDICINES, including some antibiotics or the herbal supplement St. John’s Wort, your pills may not work as well. Use a back-up method (such as condoms, spermicides, or diaphragm) until you check with your doctor or healthcare provider.

6. IF YOU HAVE TROUBLE REMEMBERING TO TAKE THE PILL, talk to your doctor or healthcare provider about how to make pill-taking easier or about using another method of birth control.

7. IF YOU HAVE ANY QUESTIONS OR ARE UNSURE ABOUT THE INFORMATION IN THIS LEAFLET, call your doctor or healthcare provider.

BEFORE YOU START TAKING YOUR PILLS

1. DECIDE WHAT TIME OF DAY YOU WANT TO TAKE YOUR PILL.

It is important to take it at about the same time every day.

2. LOOK AT YOUR PILL PACK: IT WILL HAVE 28 PILLS:

This 28 pill pack has 21 “active” [beige, orange, and pink] pills (with hormones) for Weeks 1, 2, 3 and 7 “inactive” [white] pills (without hormones) for Week 4.

3. ALSO FIND:

- where on the pack to start taking the pills,
- in what order to take the pills (follow the arrows), and
- the week numbers as shown in the picture below.

4. BE SURE YOU HAVE READY AT ALL TIMES:

- ANOTHER KIND OF BIRTH CONTROL (such as condoms, spermicides, or diaphragm) to use as a back-up in case you miss pills.
- AN EXTRA, FULL PILL PACK OF VELIVET (desogestrel and ethinyl estradiol tablets).

WHEN TO START THE FIRST PACK OF PILLS

You have a choice of which day to start taking your first pack of pills. Decide with your doctor or healthcare provider which is the best day for you. Pick a time of day which will be easy to remember.

DAY 1 START:

1. Pick the day label strip that starts with the first day of your period (this is the day you start bleeding or spotting, even if it is almost midnight when the bleeding begins).

2. Place this day label strip on the blister card above the first row of tablets.

Pick correct day label.

Example Only:

3. Take the first “active” [beige] pill of the first pack during the first 24 hours of your period.

4. You will not need to use a back-up method of birth control, since you are starting the pill at the beginning of your period.

SUNDAY START:

1. Take the first “active” [beige] pill of the first pack on the first Sunday after your period starts, even if you are still bleeding. If your period begins on Sunday, start the pack that same day.

2. Use another method of birth control as a back-up method if you have sex anytime from the Sunday you start your first pack until the next Sunday (7 days). Condoms, spermicides, or a diaphragm are good back-up methods of birth control.

WHAT TO DO DURING THE MONTH

1. TAKE ONE PILL AT THE SAME TIME EVERY DAY UNTIL THE PACK IS EMPTY.

Do not skip pills even if you are spotting or bleeding between monthly periods or feel sick to your stomach (nausea).

Do not skip pills even if you do not have sex very often.

2. WHEN YOU FINISH A PACK OR SWITCH YOUR BRAND OF PILLS:

Start the next pack on the day after your last pill. Do not wait any days between packs.

WHAT TO DO IF YOU MISS PILLS

If you MISS 1 “active” [beige, orange, or pink] pill:

1. Take it as soon as you remember. Take the next pill at your regular time. This means you may take 2 pills in 1 day.

2. You do not need to use a back-up birth control method if you have sex.

If you MISS 2 “active” [beige or orange] pills in a row in WEEK 1 OR WEEK 2 of your pack:

1. Take 2 pills on the day you remember and 2 pills the next day.

2. Then take 1 pill a day until you finish the pack.

3. You COULD BECOME PREGNANT if you have sex in the 7 days after you restart your pills. You MUST use another birth control method (such as condoms, spermicides, or diaphragm) as a back-up method for those 7 days.

If you MISS 2 “active” [pink] pills in a row in WEEK 3:

1. If you are a Day 1 Starter:

THROW OUT the rest of the pill pack and start a new pack that same day.

If you are a Sunday Starter:

Keep taking 1 pill every day until Sunday.

On Sunday, THROW OUT the rest of the pack and start a new pack of pills that same day.

2. You may not have your period this month, but this is expected. However, if you miss your period 2 months in a row, call your doctor or healthcare provider because you might be pregnant.

3. You COULD BECOME PREGNANT if you have sex in the 7 days after you restart your pills. You MUST use another birth control method (such as condoms, spermicides, or diaphragm) as a back-up method for those 7 days.

If you MISS 3 OR MORE “active” [beige, orange, or pink] pills in a row (during the first 3 weeks):

1. If you are a Day 1 Starter:

THROW OUT the rest of the pill pack and start a new pack that same day.

If you are a Sunday Starter:

Keep taking 1 pill every day until Sunday.

On Sunday, THROW OUT the rest of the pack and start a new pack of pills that same day.

2. You may not have your period this month, but this is expected. However, if you miss your period 2 months in a row, call your doctor or healthcare provider because you might be pregnant.

3. You COULD BECOME PREGNANT if you have sex on the days when you missed pills or during the first 7 days after restarting your pills. You MUST use another birth control method (such as condoms, spermicides, or diaphragm) as a back-up method the next time you have sex and for the first 7 days after you restart your pills.

IF YOU FORGET ANY OF THE 7 “INACTIVE” [WHITE] PILLS IN WEEK 4:

1. THROW AWAY the pills you missed.
2. Keep taking 1 pill each day until the pack is empty.
3. You do not need to use a back-up method of birth control.

FINALLY, IF YOU ARE STILL NOT SURE WHAT TO DO ABOUT THE PILLS YOU HAVE MISSED:

1. Use a BACK-UP METHOD of birth control anytime you have sex.
2. KEEP TAKING ONE “ACTIVE” [BEIGE, ORANGE, OR PINK] PILL EACH DAY until you can reach your doctor or healthcare provider.

ADDITIONAL INFORMATION

1. PREGNANCY DUE TO PILL FAILURE

The incidence of pill failure resulting in pregnancy is approximately one percent (i.e., one pregnancy per 100 women per year of use) if taken every day as directed, but more typical failure rates are about 5% (5 pregnancies per 100 women per year of use). If failure does occur, the risk to the fetus is minimal.

2. PREGNANCY AFTER STOPPING THE PILL

There may be some delay in becoming pregnant after you stop using oral contraceptives, especially if you had irregular menstrual cycles before you used oral contraceptives. It may be advisable to postpone conception until you begin menstruating regularly once you have stopped taking the pill and desire pregnancy.

There does not appear to be any increase in birth defects in newborn babies when pregnancy occurs soon after stopping the pill.

3. OVERDOSAGE

Serious ill effects have not been reported following ingestion of large doses of oral contraceptives by young children. Overdosage may cause nausea and withdrawal bleeding in females. In case of overdosage, contact your doctor, healthcare provider, or pharmacist.

4. OTHER INFORMATION

Your doctor or healthcare provider will take a medical and family history and may examine you before prescribing an oral contraceptive. The physical examination may be delayed to another time if you request it and your doctor or the healthcare provider believes that it is a good medical practice to postpone it. You should be reexamined at least once a year. Be sure to inform your doctor or healthcare provider if there is a family history of any of the conditions listed previously in this leaflet. Be sure to keep all appointments with your doctor or healthcare provider, because this is a time to determine if there are early signs of side effects of oral contraceptive use.

Do not use the drug for any condition other than the one for which it was prescribed. This drug has been prescribed specifically for you; do not give it to others who may want birth control pills.

HEALTH BENEFITS FROM ORAL CONTRACEPTIVES

In addition to preventing pregnancy, use of combination oral contraceptives may provide certain benefits. They are:

- menstrual cycles may become more regular
- blood flow during menstruation may be lighter and less iron may be lost. Therefore, anemia due to iron deficiency is less likely to occur
- pain or other symptoms during menstruation may be encountered less frequently
- ectopic (tubal) pregnancy may occur less frequently
- non-cancerous cysts or lumps in the breast may occur less frequently
- acute pelvic inflammatory disease may occur less frequently
- oral contraceptive use may provide some protection against developing two forms of cancer: cancer of the ovaries and cancer of the lining of the uterus

If you want more information about birth control pills, ask your doctor, healthcare provider, or pharmacist. They have a more technical leaflet called the Prescribing Information, which you may wish to read.

Call your doctor for medical advice about side effects. You may report side effects to FDA at 1-800-FDA-1088.

Store at 20° to 25°C (68° to 77°F) [See USP Controlled Room Temperature].

KEEP THIS AND ALL MEDICATIONS OUT OF THE REACH OF CHILDREN.

Brands listed are the trademarks of their respective owners.

Teva Pharmaceuticals USA, Inc.

North Wales, PA 19454

Rev. C 9/2022